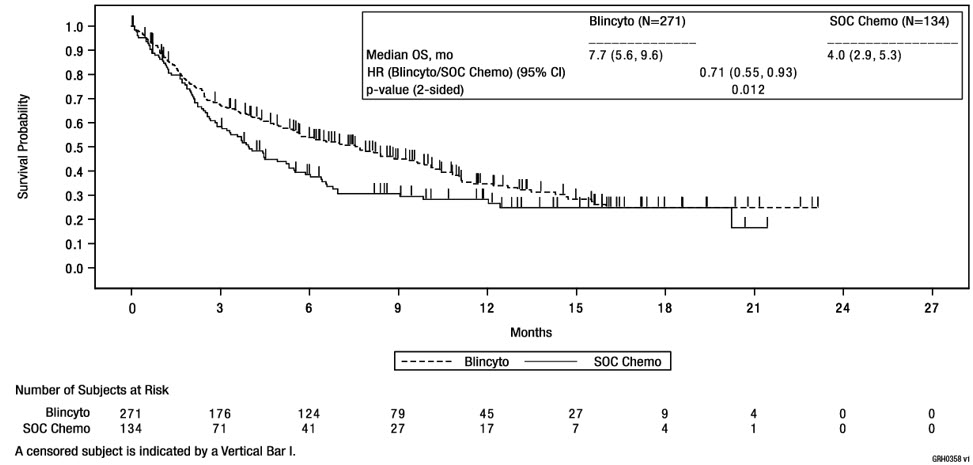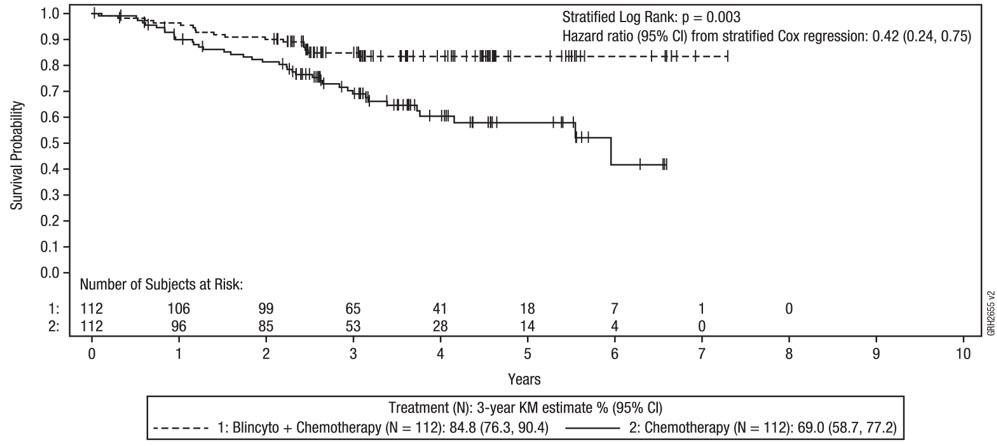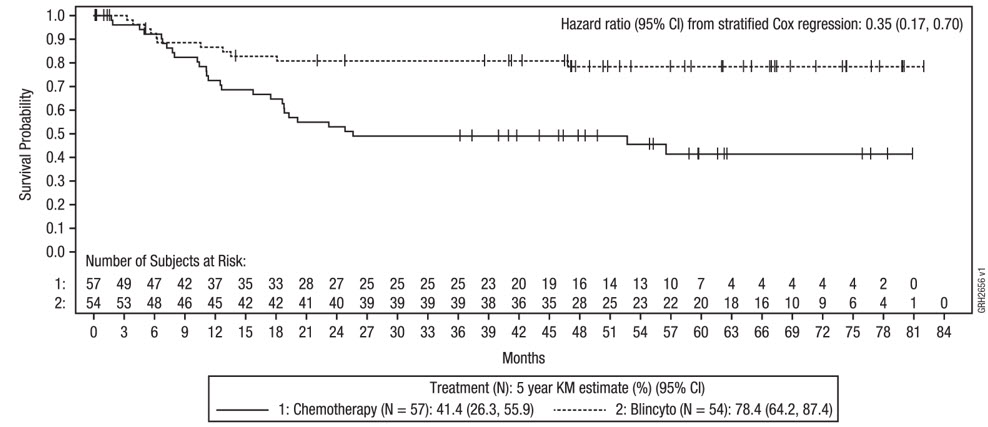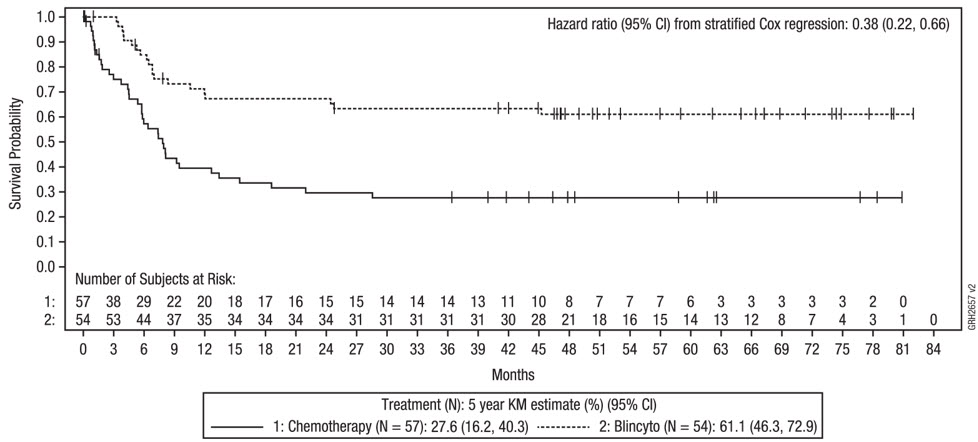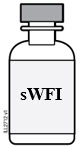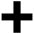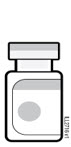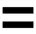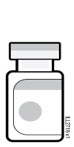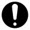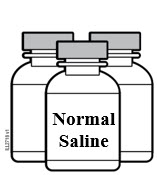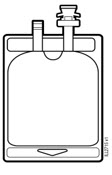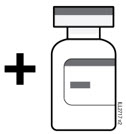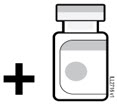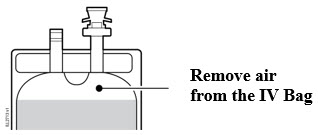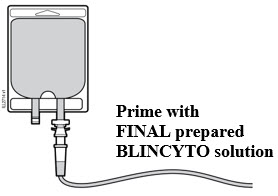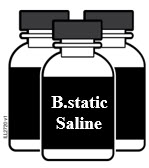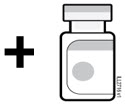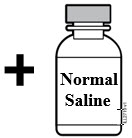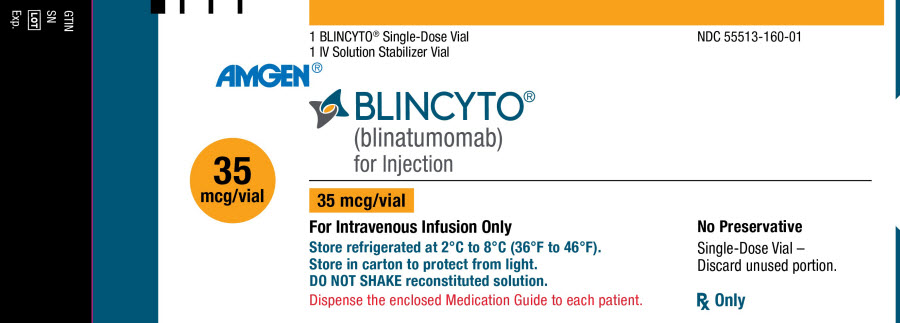 DRUG LABEL: BLINCYTO
NDC: 55513-160 | Form: KIT | Route: INTRAVENOUS
Manufacturer: Amgen, Inc
Category: prescription | Type: HUMAN PRESCRIPTION DRUG LABEL
Date: 20251021

ACTIVE INGREDIENTS: BLINATUMOMAB 12.5 ug/1 mL
INACTIVE INGREDIENTS: CITRIC ACID MONOHYDRATE 1.19 mg/1 mL; LYSINE HYDROCHLORIDE 8.27 mg/1 mL; POLYSORBATE 80 0.23 mg/1 mL; TREHALOSE DIHYDRATE 34 mg/1 mL; SODIUM HYDROXIDE; CITRIC ACID MONOHYDRATE 5.25 mg/1 mL; LYSINE HYDROCHLORIDE 228.38 mg/1 mL; POLYSORBATE 80 1 mg/1 mL; SODIUM HYDROXIDE; WATER

HIGHLIGHTS OF PRESCRIBING INFORMATION

These highlights do not include all the information needed to use BLINCYTO® safely and effectively. See full prescribing information for BLINCYTO.
BLINCYTO® (blinatumomab) for injection, for intravenous use
Initial U.S. Approval: 2014

WARNING: CYTOKINE RELEASE SYNDROME and NEUROLOGICAL TOXICITIES including IMMUNE EFFECTOR CELL-ASSOCIATED NEUROTOXICITY SYNDROME

See full prescribing information for complete boxed warning.

- Cytokine Release Syndrome (CRS), which may be life-threatening or fatal, occurred in patients receiving BLINCYTO. Interrupt or discontinue BLINCYTO and treat with corticosteroids as recommended. (2.4, 5.1)
- Neurological toxicities, including immune effector cell-associated neurotoxicity syndrome (ICANS), which may be severe, life-threatening, or fatal, occurred in patients receiving BLINCYTO. Interrupt or discontinue BLINCYTO as recommended. (2.4, 5.2)

RECENT MAJOR CHANGES

Dosage and Administration (2.1, 2.2, 2.3) | 12/2024
Dosage and Administration (2.4, 2.5, 2.6) | 12/2024
Warnings and Precautions, Cytokine Release Syndrome (5.1) | 10/2025
Warnings and Precautions, Neurological Toxicities including Immune Effector Cell-Associated Neurotoxicity (5.2) | 4/2025
Warnings and Precautions, Benzyl Alcohol Toxicity in Neonates (5.12) | 12/2024

1 INDICATIONS AND USAGE

BLINCYTO is a bispecific CD19-directed CD3 T-cell engager indicated for the treatment of adult and pediatric patients one month and older with:

- CD19-positive B-cell precursor acute lymphoblastic leukemia (ALL) in first or second complete remission with minimal residual disease (MRD) greater than or equal to 0.1%. (1.1)
- Relapsed or refractory CD19-positive B-cell precursor acute lymphoblastic leukemia (ALL). (1.2)
- CD19-positive Philadelphia chromosome-negative B-cell precursor acute lymphoblastic leukemia (ALL) in the consolidation phase of multiphase chemotherapy. (1.3)

2 DOSAGE AND ADMINISTRATION

- For the treatment of MRD-positive B-cell Precursor ALL
  - See Full Prescribing Information for recommended dose by patient weight and schedule. (2.1)
  - Hospitalization is recommended for the first 3 days of the first cycle and the first 2 days of the second cycle. (2.1)
  - Premedicate with prednisone or equivalent dexamethasone. (2.1)
- For the treatment of Relapsed or Refractory B-cell Precursor ALL
  - See Full Prescribing Information for recommended dose by patient weight and schedule. (2.2)
  - Hospitalization is recommended for the first 9 days of the first cycle and the first 2 days of the second cycle. (2.2)
  - Premedicate with dexamethasone. (2.2)
- For the treatment of B-cell Precursor ALL in the Consolidation Phase
  - See Full Prescribing Information for recommended dose by patient weight and schedule. (2.3)
  - Hospitalization is recommended for the first 3 days of the first cycle and the first 2 days of the second cycle. (2.3)
  - Premedicate with dexamethasone. (2.3)
- Refer to Full Prescribing Information for important preparation and administration information. (2.5)
- Administer as a continuous intravenous infusion at a constant flow rate using an infusion pump.
  - See Instructions for Use for infusion over 24 hours or 48 hours.
  - See Instructions for Use for infusion over 72 hours, 96 hours, or 7 days using Bacteriostatic 0.9% Sodium Chloride Injection (containing 0.9% benzyl alcohol). This option is not recommended for patients weighing less than 5.4 kg.

3 DOSAGE FORMS AND STRENGTHS

For injection: 35 mcg of lyophilized powder in a single-dose vial for reconstitution. (3)

4 CONTRAINDICATIONS

Known hypersensitivity to blinatumomab or to any component of the product formulation. (4)

5 WARNINGS AND PRECAUTIONS

- Infections: Monitor patients for signs or symptoms; treat appropriately. (5.3)
- Effects on Ability to Drive and Use Machines: Advise patients to refrain from driving and engaging in hazardous occupations or activities such as operating heavy or potentially dangerous machinery while BLINCYTO is being administered. (5.6)
- Pancreatitis: Evaluate patients who develop signs and symptoms of pancreatitis. Management of pancreatitis may require either temporary interruption or discontinuation of BLINCYTO. (5.8)
- Preparation and Administration Errors: Strictly follow instructions for preparation (including admixing) and administration. (5.10)
- Benzyl Alcohol Toxicity in Neonates: Use BLINCYTO prepared with preservative-free saline for neonates. BLINCYTO solution containing benzyl alcohol is not recommended for patients weighing less than 5.4 kg. (5.12, 8.4)
- Embryo-Fetal Toxicity: May cause fetal harm. Advise females of reproductive potential of the potential risk to the fetus and to use effective contraception. (5.13, 8.1, 8.3)

6 ADVERSE REACTIONS

The most common adverse reactions (≥ 20%) are pyrexia, infusion-related reactions, headache, infection, musculoskeletal pain, neutropenia, nausea, anemia, thrombocytopenia, and diarrhea. (6.1)

To report SUSPECTED ADVERSE REACTIONS, contact Amgen Inc. at 1-800-77-AMGEN (1-800-772-6436) or FDA at 1-800-FDA-1088 or www.fda.gov/medwatch.

FULL PRESCRIBING INFORMATION

WARNING: CYTOKINE RELEASE SYNDROME and NEUROLOGICAL TOXICITIES including IMMUNE EFFECTOR CELL-ASSOCIATED NEUROTOXICITY SYNDROME

- Cytokine Release Syndrome (CRS), which may be life-threatening or fatal, occurred in patients receiving BLINCYTO. Interrupt or discontinue BLINCYTO and treat with corticosteroids as recommended [see Dosage and Administration (2.4), Warnings and Precautions (5.1)].
- Neurological toxicities, including immune effector cell-associated neurotoxicity syndrome (ICANS) which may be severe, life-threatening, or fatal, occurred in patients receiving BLINCYTO. Interrupt or discontinue BLINCYTO as recommended [see Dosage and Administration (2.4), Warnings and Precautions (5.2)].

1 INDICATIONS AND USAGE

1.1 MRD-positive B-cell Precursor ALL

BLINCYTO is indicated for the treatment of CD19-positive B-cell precursor acute lymphoblastic leukemia (ALL) in first or second complete remission with minimal residual disease (MRD) greater than or equal to 0.1% in adult and pediatric patients one month and older.

1.2 Relapsed or Refractory B-cell Precursor ALL

BLINCYTO is indicated for the treatment of relapsed or refractory CD19-positive B-cell precursor acute lymphoblastic leukemia (ALL) in adult and pediatric patients one month and older.

1.3 B-cell Precursor ALL in the Consolidation Phase

BLINCYTO is indicated for the treatment of CD19-positive Philadelphia chromosome-negative B-cell precursor acute lymphoblastic leukemia (ALL) in the consolidation phase of multiphase chemotherapy in adult and pediatric patients one month and older.

2 DOSAGE AND ADMINISTRATION

2.1 Treatment of MRD-positive B-cell Precursor ALL

- A treatment course consists of 1 cycle of BLINCYTO for induction followed by up to 3 additional cycles for consolidation.
- A single cycle of treatment of BLINCYTO induction or consolidation consists of 28 days of continuous intravenous infusion followed by a 14-day treatment-free interval (total 42 days).
- See Table 1 for the recommended dose by patient weight and schedule. Patients weighing 45 kg or more receive a fixed-dose. For patients weighing less than 45 kg, the dose is calculated using the patient's body surface area (BSA).

Table 1. Recommended BLINCYTO Dose and Schedule for the Treatment of MRD-positive B-cell Precursor ALL
Cycle | Patients Weighing 45 kg or More (Fixed-dose) | Patients Weighing Less Than 45 kg (BSA-based dose)
Induction Cycle 1
Days 1-28 | 28 mcg/day | 15 mcg/m^2/day (not to exceed 28 mcg/day)
Days 29-42 | 14-day treatment-free interval | 14-day treatment-free interval
Consolidation Cycles 2-4
Days 1-28 | 28 mcg/day | 15 mcg/m^2/day (not to exceed 28 mcg/day)
Days 29-42 | 14-day treatment-free interval | 14-day treatment-free interval

- Hospitalization is recommended for the first 3 days of the first cycle and the first 2 days of the second cycle. For all subsequent cycle starts and re-initiations (e.g., if treatment is interrupted for 4 or more hours), supervision by a healthcare professional or hospitalization is recommended.
- Intrathecal chemotherapy prophylaxis is recommended before and during BLINCYTO therapy to prevent central nervous system ALL relapse.
- Premedicate with prednisone or equivalent for MRD-positive B-cell Precursor ALL:
  - For adult patients, premedicate with prednisone 100 mg intravenously or equivalent (e.g., dexamethasone 16 mg) 1 hour prior to the first dose of BLINCYTO in each cycle.
  - For pediatric patients, premedicate with 5 mg/m^2 of dexamethasone intravenously or orally, to a maximum dose of 20 mg, prior to the first dose of BLINCYTO in the first cycle and when restarting an infusion after an interruption of 4 or more hours in the first cycle.
- For administration of BLINCYTO:
  - See Instructions for Use for infusion over 24 hours or 48 hours.
  - See Instructions for Use for infusion over 72 hours, 96 hours, or 7 days using Bacteriostatic 0.9% Sodium Chloride Injection (containing 0.9% benzyl alcohol). The administration of BLINCYTO as a 72-hour, 96-hour, and 7-day infusion is not recommended for patients weighing less than 5.4 kg.

2.2 Treatment of Relapsed or Refractory B-cell Precursor ALL

- A treatment course consists of up to 2 cycles of BLINCYTO for induction followed by 3 additional cycles for consolidation and up to 4 additional cycles of continued therapy.
- A single cycle of treatment of BLINCYTO induction or consolidation consists of 28 days of continuous intravenous infusion followed by a 14-day treatment-free interval (total 42 days).
- A single cycle of treatment of BLINCYTO continued therapy consists of 28 days of continuous intravenous infusion followed by a 56-day treatment-free interval (total 84 days).
- See Table 2 for the recommended dose by patient weight and schedule. Patients weighing 45 kg or more receive a fixed-dose and for patients weighing less than 45 kg, the dose is calculated using the patient's BSA.

Table 2. Recommended BLINCYTO Dose and Schedule for the Treatment of Relapsed or Refractory B-cell Precursor ALL
Cycle | Patients Weighing 45 kg or More (Fixed-dose) | Patients Weighing Less Than 45 kg (BSA-based dose)
Cycle | Induction Cycle 1
Days 1-7 | 9 mcg/day | 5 mcg/m^2/day (not to exceed 9 mcg/day)
Days 8-28 | 28 mcg/day | 15 mcg/m^2/day (not to exceed 28 mcg/day)
Days 29-42 | 14-day treatment-free interval | 14-day treatment-free interval
Induction Cycle 2
Days 1-28 | 28 mcg/day | 15 mcg/m^2/day (not to exceed 28 mcg/day)
Days 29-42 | 14-day treatment-free interval | 14-day treatment-free interval
Consolidation Cycles 3-5
Days 1-28 | 28 mcg/day | 15 mcg/m^2/day (not to exceed 28 mcg/day)
Days 29-42 | 14-day treatment-free interval | 14-day treatment-free interval
Continued Therapy Cycles 6-9
Days 1-28 | 28 mcg/day | 15 mcg/m^2/day (not to exceed 28 mcg/day)
Days 29-84 | 56-day treatment-free interval | 56-day treatment-free interval

- Hospitalization is recommended for the first 9 days of the first cycle and the first 2 days of the second cycle. For all subsequent cycle starts and re-initiations (e.g., if treatment is interrupted for 4 or more hours), supervision by a healthcare professional or hospitalization is recommended.
- Intrathecal chemotherapy prophylaxis is recommended before and during BLINCYTO therapy to prevent central nervous system ALL relapse.
- Premedicate with dexamethasone:
  - For adult patients, premedicate with 20 mg of dexamethasone intravenously or orally 1 hour prior to the first dose of BLINCYTO of each cycle, prior to a step dose (such as Cycle 1 Day 8), and when restarting an infusion after an interruption of 4 or more hours.
  - For pediatric patients, premedicate with 5 mg/m^2 of dexamethasone intravenously or orally, to a maximum dose of 20 mg, prior to the first dose of BLINCYTO in the first cycle, prior to a step dose (such as Cycle 1 Day 8), and when restarting an infusion after an interruption of 4 or more hours in the first cycle.
- For administration of BLINCYTO:
  - See Instructions for Use for infusion over 24 hours or 48 hours.
  - See Instructions for Use for infusion over 72 hours, 96 hours, or 7 days using Bacteriostatic 0.9% Sodium Chloride Injection (containing 0.9% benzyl alcohol). The administration of BLINCYTO as a 72-hour, 96-hour, and 7-day infusion is not recommended for patients weighing less than 5.4 kg.

2.3 Treatment of B-cell Precursor ALL in the Consolidation Phase

- A single cycle of BLINCYTO monotherapy in consolidation is 28 days of continuous infusion followed by a 14-day treatment-free interval (total 42 days) [see Table 3 and Clinical Studies (14.3)].
- Patients weighing 45 kg or more receive a fixed-dose, and for patients weighing less than 45 kg, the dose is calculated using the patient's BSA (see Table 3).

Table 3. Recommended BLINCYTO Dose and Schedule in the Consolidation Phase of Treatment of B-cell Precursor ALL
BLINCYTO Consolidation Cycle | Patients Weighing 45 kg or More (Fixed-dose) | Patients Weighing Less Than 45 kg (BSA-based dose)
Days 1-28 | 28 mcg/day | 15 mcg/m^2/day (not to exceed 28 mcg/day)
Days 29-42 | 14-day treatment-free interval | 14-day treatment-free interval

- Hospitalization is recommended for the first 3 days of the first cycle and the first 2 days of the second cycle. For all subsequent cycle starts and re-initiations (e.g., if treatment is interrupted for 4 or more hours), supervision by a healthcare professional or hospitalization is recommended.
- Intrathecal chemotherapy prophylaxis is recommended before and during BLINCYTO therapy to prevent central nervous system ALL relapse.
- Premedicate with dexamethasone:
  - For adult patients, premedicate with dexamethasone 20 mg intravenously within 1 hour prior to the first dose of BLINCYTO of each cycle.
  - For pediatric patients, premedicate with 5 mg/m^2 of dexamethasone intravenously or orally, to a maximum dose of 20 mg prior to the first dose of BLINCYTO in the first cycle and when restarting an infusion after an interruption of 4 or more hours in the first cycle.
- For administration of BLINCYTO:
  - See Instructions for Use for infusion over 24 hours or 48 hours.
  - See Instructions for Use for infusion over 72 hours, 96 hours, or 7 days using Bacteriostatic 0.9% Sodium Chloride Injection (containing 0.9% benzyl alcohol). The administration of BLINCYTO as a 72-hour, 96-hour, and 7-day infusion is not recommended for patients weighing less than 5.4 kg.

2.4 Dosage Modifications for Adverse Reactions

If the interruption after an adverse reaction is no longer than 7 days, continue the same cycle to a total of 28 days of infusion inclusive of days before and after the interruption in that cycle. If an interruption due to an adverse reaction is longer than 7 days, start a new cycle.

Table 4. Dosage Modifications for Adverse Reactions
Adverse Reaction | Grade [Based on the Common Terminology Criteria for Adverse Events (CTCAE). Grade 3 is severe, and Grade 4 is life-threatening.] | Patients Weighing 45 kg or More | Patients Weighing Less Than 45 kg
Cytokine Release Syndrome (CRS) | Grade 3 | - Interrupt BLINCYTO. - Administer dexamethasone 8 mg every 8 hours intravenously or orally for up to 3 days and taper thereafter over 4 days. - When CRS is resolved, restart BLINCYTO at 9 mcg/day, and escalate to 28 mcg/day after 7 days if the adverse reaction does not recur. | - Interrupt BLINCYTO. - Administer dexamethasone 5 mg/m^2 (maximum 8 mg) every 8 hours intravenously or orally for up to 3 days and taper thereafter over 4 days. - When CRS is resolved, restart BLINCYTO at 5 mcg/m^2/day, and escalate to 15 mcg/m^2/day after 7 days if the adverse reaction does not recur.
 | Grade 4 | Discontinue BLINCYTO permanently. Administer dexamethasone as instructed for Grade 3 CRS.
Neurological Toxicity | Seizure | Discontinue BLINCYTO permanently if more than one seizure occurs.
 | Grade 2 ICANS | Interrupt BLINCYTO until ICANS resolves. Administer corticosteroids and manage according to current practice guidelines. When ICANS is resolved, restart BLINCYTO at 9 mcg/day. Escalate to 28 mcg/day after 7 days if the adverse reaction does not recur. | Interrupt BLINCYTO until ICANS resolves. Administer corticosteroids and manage according to current practice guidelines. When ICANS is resolved, restart BLINCYTO at 5 mcg/m^2/day. Escalate to 15 mcg/m^2/day after 7 days if the adverse reaction does not recur.
 | Grade 3 Neurologic Events including ICANS | Withhold BLINCYTO until no more than Grade 1 (mild) and for at least 3 days, then restart BLINCYTO at 9 mcg/day. Escalate to 28 mcg/day after 7 days if the adverse reaction does not recur. If the adverse reaction occurred at 9 mcg/day, or if the adverse reaction takes more than 7 days to resolve, discontinue BLINCYTO permanently. | Withhold BLINCYTO until no more than Grade 1 (mild) and for at least 3 days, then restart BLINCYTO at 5 mcg/m^2/day. Escalate to 15 mcg/m^2/day after 7 days if the adverse reaction does not recur. If the adverse reaction occurred at 5 mcg/m^2/day, or if the adverse reaction takes more than 7 days to resolve, discontinue BLINCYTO permanently.
 |  | If ICANS, administer corticosteroids and manage according to current practice guidelines.
 | Grade 4 | Discontinue BLINCYTO permanently.
 | Neurologic Events including ICANS | If ICANS, administer corticosteroids and manage according to current practice guidelines.
Other Clinically Relevant Adverse Reactions | Grade 3 | Withhold BLINCYTO until no more than Grade 1 (mild), then restart BLINCYTO at 9 mcg/day. Escalate to 28 mcg/day after 7 days if the adverse reaction does not recur. If the adverse reaction takes more than 14 days to resolve, discontinue BLINCYTO permanently. | Withhold BLINCYTO until no more than Grade 1 (mild), then restart BLINCYTO at 5 mcg/m^2/day. Escalate to 15 mcg/m^2/day after 7 days if the adverse reaction does not recur. If the adverse reaction takes more than 14 days to resolve, discontinue BLINCYTO permanently.
 | Grade 4 | Consider discontinuing BLINCYTO permanently.

2.5 Preparation and Administration of BLINCYTO

It is very important that the instructions for preparation (including admixing) and administration provided in this section are strictly followed to minimize medication errors (including underdose and overdose) [see Warnings and Precautions (5.10)].

BLINCYTO can be infused over 24 hours (preservative-free), 48 hours (preservative-free), 72 hours (with preservative), 96 hours (with preservative), or 7 days (with preservative). The choice between these options for the infusion duration should be made by the treating healthcare provider considering the frequency of the infusion bag changes and the weight of the patient. The administration of BLINCYTO as a 72-hour, 96-hour, and 7-day infusion is not recommended for patients weighing less than 5.4 kg.

For preparation, reconstitution, and administration of BLINCYTO:

The BLINCYTO Instructions for Use contains more detailed instructions on the preparation of infusion [see Instructions for Use].

The preparation steps differ based on the infusion duration. Follow the steps specific to the infusion duration you are preparing.

Parenteral drug products should be inspected visually for particulate matter and discoloration prior to administration, whenever solution and container permit.

Call 1-800-77-AMGEN (1-800-772-6436) if you have questions about the reconstitution and preparation of BLINCYTO.

2.6 Storage of Reconstituted BLINCYTO

The information in Table 5 indicates the storage time for the reconstituted BLINCYTO vial and prepared infusion bag.

Table 5. Storage Time for Reconstituted BLINCYTO Vial and Prepared BLINCYTO Infusion Bag
 | Maximum Storage Time
 | Room Temperature 23°C to 27°C (73°F to 81°F) | Refrigerated 2°C to 8°C (36°F to 46°F)
Reconstituted BLINCYTO Vial | 4 hours | 24 hours
Prepared BLINCYTO 24-Hour and 48-Hour Infusion Bag (Preservative-free) | 48 hours [Storage time includes infusion time. If the prepared BLINCYTO infusion bag is not administered within the time frames and temperatures indicated, it must be discarded; it should not be refrigerated again.] | 8 days
Prepared BLINCYTO 72-Hour and 96-Hour Infusion Bag (with Preservative) | 4 days | 14 days
Prepared BLINCYTO 7-Day Infusion Bag (with Preservative) | 7 days | 14 days

3 DOSAGE FORMS AND STRENGTHS

For injection: 35 mcg of white to off-white lyophilized powder in a single-dose vial for reconstitution.

4 CONTRAINDICATIONS

BLINCYTO is contraindicated in patients with known hypersensitivity to blinatumomab or to any component of the product formulation.

5 WARNINGS AND PRECAUTIONS

5.1 Cytokine Release Syndrome

Cytokine Release Syndrome (CRS), which may be life-threatening or fatal, occurred in patients receiving BLINCYTO. The median time to onset of CRS was 2 days after the start of infusion and the median time to resolution of CRS was 5 days among cases that resolved. Manifestations of CRS include fever, headache, nausea, asthenia, hypotension, increased alanine aminotransferase (ALT), increased aspartate aminotransferase (AST), increased total bilirubin, and disseminated intravascular coagulation (DIC). The manifestations of CRS after treatment with BLINCYTO overlap with those of infusion reactions, capillary leak syndrome (CLS), and hemophagocytic lymphohistiocytosis (HLH)/macrophage activation syndrome (MAS). Evaluation for HLH/MAS should be considered when CRS is atypical or prolonged, or when features of macrophage activation are present. Using all of these terms to define CRS in clinical trials of BLINCYTO, CRS was reported in 15% of patients with relapsed or refractory ALL, in 7% of patients with MRD-positive ALL, and in 16% of patients receiving BLINCYTO cycles in the consolidation phase of therapy [see Adverse Reactions (6.1)].

Monitor patients for signs or symptoms of these events. Advise outpatients on BLINCYTO to contact their healthcare professional for signs and symptoms associated with CRS. If severe CRS occurs, interrupt BLINCYTO until CRS resolves. Discontinue BLINCYTO permanently if life-threatening CRS occurs. Administer corticosteroids for severe or life-threatening CRS [see Dosage and Administration (2.4)].

5.2 Neurological Toxicities, including Immune Effector Cell-Associated Neurotoxicity Syndrome

BLINCYTO can cause serious or life-threatening neurologic toxicity, including ICANS [see Adverse Reactions 6.1].

The incidence of neurologic toxicities in clinical trials was approximately 65% [see Adverse Reactions (6.1)]. Among patients that experienced a neurologic toxicity, the median time to the first event was within the first 2 weeks of BLINCYTO treatment. The most common (≥ 10%) manifestations of neurological toxicity were headache, and tremor; the neurological toxicity profile varied by age group [see Use in Specific Populations (8.4, 8.5)]. Grade 3 or higher neurological toxicities following initiation of BLINCYTO administration occurred in approximately 13% of patients and included encephalopathy, convulsions, speech disorders, disturbances in consciousness, confusion and disorientation, and coordination and balance disorders. Manifestations of neurological toxicity included cranial nerve disorders. The majority of neurologic toxicities resolved following interruption of BLINCYTO, but some resulted in treatment discontinuation.

The incidence of signs and symptoms consistent with ICANS in clinical trials was 7.5%. The onset of ICANS can be concurrent with CRS, following resolution of CRS, or in the absence of CRS.

There is limited experience with BLINCYTO in patients with active ALL in the central nervous system (CNS) or a history of neurologic events. Patients with a history or presence of clinically relevant CNS pathology were excluded from clinical studies. Patients with Down Syndrome may have a higher risk of seizures with BLINCYTO therapy; consider seizure prophylaxis prior to initiation of BLINCYTO for these patients.

Monitor patients receiving BLINCYTO for signs and symptoms of neurological toxicities, including ICANS. Advise outpatients on BLINCYTO to contact their healthcare professional if they develop signs or symptoms of neurological toxicities. Management of neurologic toxicity may require interruption or discontinuation of BLINCYTO as recommended and/or treatment with corticosteroids [see Dosage and Administration (2.4)].

5.3 Infections

In patients with ALL receiving BLINCYTO in clinical studies, serious infections such as sepsis, pneumonia, bacteremia, opportunistic infections, and catheter-site infections were observed in approximately 25% of patients, some of which were life-threatening or fatal [see Adverse Reactions (6.1)]. As appropriate, administer prophylactic antibiotics and employ surveillance testing during treatment with BLINCYTO. Monitor patients for signs and symptoms of infection and treat appropriately.

5.4 Tumor Lysis Syndrome

Tumor lysis syndrome (TLS), which may be life-threatening or fatal, has been observed in patients receiving BLINCYTO [see Adverse Reactions (6.1)]. Appropriate prophylactic measures, including pretreatment nontoxic cytoreduction and on-treatment hydration, should be used for the prevention of TLS during BLINCYTO treatment. Monitor for signs or symptoms of TLS. Management of these events may require either temporary interruption or discontinuation of BLINCYTO [see Dosage and Administration (2.4)].

5.5 Neutropenia and Febrile Neutropenia

Neutropenia and febrile neutropenia, including life-threatening cases, have been observed in patients receiving BLINCYTO [see Adverse Reactions (6.1)]. Monitor laboratory parameters (including, but not limited to, white blood cell count and absolute neutrophil count) during BLINCYTO infusion. Interrupt BLINCYTO if prolonged neutropenia occurs.

5.6 Effects on Ability to Drive and Use Machines

Due to the potential for neurologic events, including seizures and ICANS, patients receiving BLINCYTO are at risk for loss of consciousness [see Warnings and Precautions (5.2)]. Advise patients to refrain from driving and engaging in hazardous occupations or activities such as operating heavy or potentially dangerous machinery while BLINCYTO is being administered.

5.7 Elevated Liver Enzymes

Treatment with BLINCYTO was associated with transient elevations in liver enzymes [see Adverse Reactions (6.1)]. In patients with ALL receiving BLINCYTO in clinical studies, the median time to onset of elevated liver enzymes was 3 days.

The majority of these transient elevations in liver enzymes were observed in the setting of CRS. For the events that were observed outside the setting of CRS, the median time to onset was 19 days. Grade 3 or greater elevations in liver enzymes occurred in approximately 7% of patients outside the setting of CRS and resulted in treatment discontinuation in less than 1% of patients.

Monitor alanine aminotransferase (ALT), aspartate aminotransferase (AST), gamma-glutamyl transferase (GGT), and total blood bilirubin prior to the start of and during BLINCYTO treatment. Interrupt BLINCYTO if the transaminases rise to greater than 5 times the upper limit of normal or if total bilirubin rises to more than 3 times the upper limit of normal.

5.8 Pancreatitis

Fatal pancreatitis has been reported in patients receiving BLINCYTO in combination with dexamethasone in clinical studies and the postmarketing setting [see Adverse Reactions (6.2)].

Evaluate patients who develop signs and symptoms of pancreatitis. Management of pancreatitis may require either temporary interruption or discontinuation of BLINCYTO and dexamethasone [see Dosage and Administration (2.4)].

5.9 Leukoencephalopathy

Cranial magnetic resonance imaging (MRI) changes showing leukoencephalopathy have been observed in patients receiving BLINCYTO, especially in patients with prior treatment with cranial irradiation and antileukemic chemotherapy (including systemic high-dose methotrexate or intrathecal cytarabine). The clinical significance of these imaging changes is unknown.

5.10 Preparation and Administration Errors

Preparation and administration errors have occurred with BLINCYTO treatment. Follow instructions for preparation (including admixing) and administration strictly to minimize medication errors (including underdose and overdose) [see Dosage and Administration (2.5) and Instructions for Use].

5.11 Immunization

The safety of immunization with live viral vaccines during or following BLINCYTO therapy has not been studied. Vaccination with live virus vaccines is not recommended for at least 2 weeks prior to the start of BLINCYTO treatment, during treatment, and until immune recovery following last cycle of BLINCYTO.

5.12 Benzyl Alcohol Toxicity in Neonates

Serious adverse reactions, including fatal reactions and the "gasping syndrome," have been reported in very low birth weight (VLBW) neonates born weighing less than 1500 g, and early preterm neonates (infants born less than 34 weeks gestational age) who received intravenous drugs containing benzyl alcohol as a preservative. Early preterm VLBW neonates may be more likely to develop these reactions, because they may be less able to metabolize benzyl alcohol [see Use in Specific Populations (8.4)].

Use the preservative-free preparations of BLINCYTO where possible in neonates. When prescribing BLINCYTO (with preservative) for neonatal patients, consider the combined daily metabolic load of benzyl alcohol from all sources including BLINCYTO (with preservative), other products containing benzyl alcohol or other excipients (e.g., ethanol, propylene glycol) which compete with benzyl alcohol for the same metabolic pathway.

Monitor neonatal patients receiving BLINCYTO (with preservative) for new or worsening metabolic acidosis. The minimum amount of benzyl alcohol at which serious adverse reactions may occur in neonates is not known. The BLINCYTO 72-Hour bag (with preservative) and 96-Hour bag (with preservative) contain 2.5 mg of benzyl alcohol per mL, and the 7-Day bag (with preservative) contains 7.4 mg of benzyl alcohol per mL. The administration of BLINCYTO as a 72-hour, 96-hour, and 7-day infusion is not recommended for patients weighing less than 5.4 kg [see Use in Specific Populations (8.4)].

5.13 Embryo-Fetal Toxicity

Based on its mechanism of action, BLINCYTO may cause fetal harm when administered to a pregnant woman. Advise pregnant women of the potential risk to the fetus. Advise females of reproductive potential to use effective contraception during treatment with BLINCYTO and for 48 hours after the last dose [see Use in Specific Populations (8.1, 8.3)].

6 ADVERSE REACTIONS

The following clinically significant adverse reactions are described elsewhere in the labeling:

- Cytokine Release Syndrome [see Warnings and Precautions (5.1)]
- Neurological Toxicities, including Immune Effector Cell-Associated Neurotoxicity Syndrome [see Warnings and Precautions (5.2)]
- Infections [see Warnings and Precautions (5.3)]
- Tumor Lysis Syndrome [see Warnings and Precautions (5.4)]
- Neutropenia and Febrile Neutropenia [see Warnings and Precautions (5.5)]
- Effects on Ability to Drive and Use Machines [see Warnings and Precautions (5.6)]
- Elevated Liver Enzymes [see Warnings and Precautions (5.7)]
- Pancreatitis [see Warnings and Precautions (5.8)]
- Leukoencephalopathy [see Warnings and Precautions (5.9)]

6.1 Clinical Trials Experience

Because clinical trials are conducted under widely varying conditions, adverse reaction rates observed in the clinical trials of a drug cannot be directly compared to rates in the clinical trials of another drug and may not reflect the rates observed in practice.

The safety of BLINCYTO in adult and pediatric patients one month and older with MRD-positive B-cell precursor ALL (n = 137), relapsed or refractory B-cell precursor ALL (n = 267), and Philadelphia chromosome-negative B-cell precursor ALL in consolidation (n = 165) was evaluated in clinical studies. The most common adverse reactions (≥ 20%) to BLINCYTO in this pooled population were pyrexia, infusion-related reactions, headache, infection, musculoskeletal pain, neutropenia, nausea, anemia, thrombocytopenia, and diarrhea.

MRD-positive B-cell Precursor ALL

The safety of BLINCYTO in patients with MRD-positive B-cell precursor ALL was evaluated in two single-arm clinical studies in which 137 adult patients were treated with BLINCYTO. The median age of the study population was 45 years (range: 18 to 77 years).

The most common adverse reactions (≥ 20%) were pyrexia, infusion-related reactions, headache, infections (pathogen unspecified), tremor, and chills. Serious adverse reactions were reported in 61% of patients. The most common serious adverse reactions (≥ 2%) included pyrexia, tremor, encephalopathy, aphasia, lymphopenia, neutropenia, overdose, device related infection, seizure, and staphylococcal infection. Adverse reactions of Grade 3 or higher were reported in 64% of patients. Discontinuation of therapy due to adverse reactions occurred in 17% of patients; neurologic events were the most frequently reported reasons for discontinuation. There were 2 fatal adverse reactions that occurred within 30 days of the end of BLINCYTO treatment (atypical pneumonia and subdural hemorrhage).

Table 6 summarizes the adverse reactions occurring at a ≥ 10% incidence for any grade or ≥ 5% incidence for Grade 3 or higher.

Table 6. Adverse Reactions Occurring at ≥ 10% Incidence for Any Grade or ≥ 5% Incidence for Grade 3 or Higher in BLINCYTO-treated Adult Patients with MRD-Positive B-cell Precursor ALL
Adverse Reaction | BLINCYTO (N = 137)
 | Any Grade [Grading based on NCI Common Terminology Criteria for Adverse Events (CTCAE) version 4.0.] n (%) | Grade ≥ 3 n (%)
Blood and lymphatic system disorders
Neutropenia [Neutropenia includes febrile neutropenia, neutropenia, and neutrophil count decreased.] | 21 (15) | 21 (15)
Leukopenia [Leukopenia includes leukopenia and white blood cell count decreased.] | 19 (14) | 13 (9)
Thrombocytopenia [Thrombocytopenia includes platelet count decreased and thrombocytopenia.] | 14 (10) | 8 (6)
Cardiac disorders
Arrhythmia [Arrhythmia includes bradycardia, sinus arrhythmia, sinus bradycardia, sinus tachycardia, tachycardia and ventricular extrasystoles.] | 17 (12) | 3 (2)
General disorders and administration site conditions
Pyrexia [Pyrexia includes body temperature increased and pyrexia.] | 125 (91) | 9 (7)
Chills | 39 (28) | 0 (0)
Infections and infestations
Infections - pathogen unspecified | 53 (39) | 11 (8)
Injury, poisoning and procedural complications
Infusion-related reaction [Infusion-related reaction is a composite term that includes the term infusion-related reaction and the following events occurring with the first 48 hours of infusion and the event lasted ≤ 2 days: cytokine release syndrome, eye swelling, hypertension, hypotension, myalgia, periorbital edema, pruritus generalized, pyrexia, and rash.] | 105 (77) | 7 (5)
Investigations
Decreased immunoglobulins [Decreased immunoglobulins includes blood immunoglobulin A decreased, blood immunoglobulin G decreased, blood immunoglobulin M decreased, hypogammaglobulinemia, hypoglobulinemia, and immunoglobulins decreased.] | 25 (18) | 7 (5)
Weight increased | 14 (10) | 1 (< 1)
Hypertransaminasemia [Hypertransaminasemia includes alanine aminotransferase increased, aspartate aminotransferase increased, and hepatic enzyme increased.] | 13 (9) | 9 (7)
Musculoskeletal and connective tissue disorders
Back pain | 16 (12) | 1 (< 1)
Nervous system disorders
Headache [May represent ICANS.] | 54 (39) | 5 (4)
Tremor, [Tremor includes essential tremor, intention tremor, and tremor.] | 43 (31) | 6 (4)
Aphasia | 16 (12) | 1 (< 1)
Dizziness | 14 (10) | 1 (< 1)
Encephalopathy, [Encephalopathy includes cognitive disorder, depressed level of consciousness, disturbance in attention, encephalopathy, lethargy, leukoencephalopathy, memory impairment, somnolence, and toxic encephalopathy.] | 14 (10) | 6 (4)
Psychiatric disorders
Insomnia, [Insomnia includes initial insomnia, insomnia, and terminal insomnia.] | 24 (18) | 1 (< 1)
Respiratory, thoracic and mediastinal disorders
Cough | 18 (13) | 0 (0)
Skin and subcutaneous tissue disorders
Rash [Rash includes dermatitis contact, eczema, erythema, rash, and rash maculopapular.] | 22 (16) | 1 (< 1)
Vascular disorders
Hypotension | 19 (14) | 1 (< 1)

Additional adverse reactions in adult patients with MRD-positive ALL that did not meet the threshold criteria for inclusion in Table 6 were:

Blood and lymphatic system disorders: anemia

General disorders and administration site conditions: edema peripheral, pain, and chest pain (includes chest pain and musculoskeletal chest pain)

Hepatobiliary disorders: blood bilirubin increased

Immune system disorders: hypersensitivity and cytokine release syndrome

Infections and infestations: viral infectious disorders, bacterial infectious disorders, and fungal infectious disorders

Injury, poisoning and procedural complications: medication error and overdose (includes overdose and accidental overdose)

Investigations: blood alkaline phosphatase increased

Musculoskeletal and connective tissue disorders: pain in extremity and bone pain

Nervous system disorders: seizure (includes seizure and generalized tonic-clonic seizure), speech disorder, and hypoesthesia

Psychiatric disorders: confusional state, disorientation, and depression

Respiratory, thoracic and mediastinal disorders: dyspnea and productive cough

Vascular disorders: hypertension (includes blood pressure increased and hypertension) flushing (includes flushing and hot flush), and capillary leak syndrome

Relapsed or Refractory B-cell Precursor ALL

The safety of BLINCYTO was evaluated in a randomized, open-label, active-controlled clinical study (TOWER Study) in which 376 adult patients with Philadelphia chromosome-negative relapsed or refractory B-cell precursor ALL were treated with BLINCYTO (n = 267) or standard of care (SOC) chemotherapy (n = 109). The median age of BLINCYTO-treated patients was 37 years (range: 18 to 80 years), 60% were male, 84% were White, 7% Asian, 2% were Black or African American, 2% were American Indian or Alaska Native, and 5% were Multiple/Other.

The most common adverse reactions (≥ 20%) in the BLINCYTO arm were infections (bacterial and pathogen unspecified), pyrexia, headache, infusion-related reactions, anemia, febrile neutropenia, thrombocytopenia, and neutropenia. Serious adverse reactions were reported in 62% of patients. The most common serious adverse reactions (≥ 2%) included febrile neutropenia, pyrexia, sepsis, pneumonia, overdose, septic shock, CRS, bacterial sepsis, device related infection, and bacteremia. Adverse reactions of Grade 3 or higher were reported in 87% of patients. Discontinuation of therapy due to adverse reactions occurred in 12% of patients treated with BLINCYTO; neurologic events and infections were the most frequently reported reasons for discontinuation of treatment due to an adverse reaction. Fatal adverse events occurred in 16% of patients. The majority of the fatal events were infections.

The adverse reactions occurring at a ≥ 10% incidence for any grade or ≥ 5% incidence for Grade 3 or higher in the BLINCYTO-treated patients in first cycle of therapy are summarized in Table 7.

Table 7. Adverse Reactions Occurring at ≥ 10% Incidence for Any Grade or ≥ 5% Incidence for Grade 3 or Higher in BLINCYTO-Treated Patients in First Cycle of Therapy for Adult Patients with Relapsed or Refractory B-cell Precursor ALL (TOWER Study)
Adverse Reaction | BLINCYTO (N = 267) |  | Standard of Care (SOC) Chemotherapy (N = 109)
Adverse Reaction | Any Grade [Grading based on NCI Common Terminology Criteria for Adverse Events (CTCAE) version 4.0.] n (%) | Grade ≥ 3 n (%) | Any Grade n (%) | Grade ≥ 3 n (%)
Blood and lymphatic system disorders
Neutropenia [Neutropenia includes agranulocytosis, febrile neutropenia, neutropenia, and neutrophil count decreased.] | 84 (31) | 76 (28) | 67 (61) | 61 (56)
Anemia [Anemia includes anemia and hemoglobin decreased.] | 68 (25) | 52 (19) | 45 (41) | 37 (34)
Thrombocytopenia [Thrombocytopenia includes platelet count decreased and thrombocytopenia.] | 57 (21) | 47 (18) | 42 (39) | 40 (37)
Leukopenia [Leukopenia includes leukopenia and white blood cell count decreased.] | 21 (8) | 18 (7) | 9 (8) | 9 (8)
Cardiac disorders
Arrhythmia [Arrhythmia includes arrhythmia, atrial fibrillation, atrial flutter, bradycardia, sinus bradycardia, sinus tachycardia, supraventricular tachycardia, and tachycardia.] | 37 (14) | 5 (2) | 18 (17) | 0 (0)
General disorders and administration site conditions
Pyrexia | 147 (55) | 15 (6) | 43 (39) | 4 (4)
Edema [Edema includes face edema, fluid retention, edema, edema peripheral, peripheral swelling, and swelling face.] | 48 (18) | 3 (1) | 20 (18) | 1 (1)
Immune system disorders
Cytokine release syndrome [Cytokine release syndrome includes cytokine release syndrome and cytokine storm.] | 37 (14) | 8 (3) | 0 (0) | 0 (0)
Infections and infestations
Infections - pathogen unspecified | 74 (28) | 40 (15) | 50 (46) | 35 (32)
Bacterial infectious disorders | 38 (14) | 19 (7) | 35 (32) | 21 (19)
Viral infectious disorders | 30 (11) | 4 (1) | 14 (13) | 0 (0)
Fungal infectious disorders | 27 (10) | 13 (5) | 15 (14) | 9 (8)
Injury, poisoning and procedural complications
Infusion-related reaction [Infusion-related reaction is a composite term that includes the term infusion-related reaction and the following events occurring with the first 48 hours of infusion and the event lasted ≤ 2 days: pyrexia, cytokine release syndrome, hypotension, myalgia, acute kidney injury, hypertension, and rash erythematous.] | 79 (30) | 9 (3) | 9 (8) | 1 (1)
Investigations
Hypertransaminasemia [Hypertransaminasemia includes alanine aminotransferase increased, aspartate aminotransferase increased, hepatic enzyme increased, and transaminases increased.] | 40 (15) | 22 (8) | 13 (12) | 7 (6)
Nervous system disorders
Headache [May represent ICANS.] | 61 (23) | 1 (< 1) | 30 (28) | 3 (3)
Skin and subcutaneous tissue disorders
Rash [Rash includes erythema, rash, rash erythematous, rash generalized, rash macular, rash maculo-papular, rash pruritic, skin exfoliation, and toxic skin eruption.] | 31 (12) | 2 (1) | 21 (19) | 0 (0)

Selected laboratory abnormalities worsening from baseline Grade 0-2 to treatment-related maximal Grade 3-4 in first cycle of therapy are shown in Table 8.

Table 8. Selected Laboratory Abnormalities Worsening from Baseline Grade 0-2 to Treatment-related Maximal Grade 3-4 [Includes only patients who had both baseline and at least one laboratory measurement during first cycle of therapy available.] in First Cycle of Therapy for Adult Patients with Relapsed or Refractory B-cell Precursor ALL (TOWER Study)
 | BLINCYTO Grade 3 or 4 (%) | SOC Chemotherapy Grade 3 or 4 (%)
Hematology
Decreased lymphocyte count | 80 | 83
Decreased white blood cell count | 53 | 97
Decreased hemoglobin | 29 | 43
Decreased neutrophil count | 57 | 68
Decreased platelet count | 47 | 85
Chemistry
Increased ALT | 11 | 11
Increased bilirubin | 5 | 4
Increased AST | 8 | 4

Other important adverse reactions from pooled relapsed or refractory B-cell precursor ALL studies were:

Blood and lymphatic system disorders: lymphadenopathy, hemophagocytic lymphohistiocytosis, and leukocytosis (includes leukocytosis and white blood cell count increased)

General disorders and administration site conditions: chills, chest pain (includes chest discomfort, chest pain, musculoskeletal chest pain, and non-cardiac chest pain), pain, body temperature increased, hyperthermia, and systemic inflammatory response syndrome

Hepatobiliary disorders: hyperbilirubinemia (includes blood bilirubin increased and hyperbilirubinemia)

Immune system disorders: hypersensitivity (includes hypersensitivity, anaphylactic reaction, angioedema, dermatitis allergic, drug eruption, drug hypersensitivity, erythema multiforme, and urticaria)

Injury, poisoning and procedural complications: medication error and overdose (includes overdose, medication error, and accidental overdose)

Investigations: weight increased, decreased immunoglobulins (includes immunoglobulins decreased, blood immunoglobulin A decreased, blood immunoglobulin G decreased, blood immunoglobulin M decreased, and hypogammaglobulinemia), blood alkaline phosphatase increased, and hypertransaminasemia

Metabolism and nutrition disorders: tumor lysis syndrome

Musculoskeletal and connective tissue disorders: back pain, bone pain, and pain in extremity

Nervous system disorders: tremor (resting tremor, intention tremor, essential tremor, and tremor), altered state of consciousness (includes altered state of consciousness, depressed level of consciousness, disturbance in attention, lethargy, mental status changes, stupor, and somnolence), dizziness, memory impairment, seizure (includes seizure, and atonic seizure), aphasia, cognitive disorder, speech disorder, hypoesthesia, encephalopathy, paresthesia, and cranial nerve disorders (trigeminal neuralgia, trigeminal nerve disorder, sixth nerve paralysis, cranial nerve disorder, facial nerve disorder, and facial paresis)

Psychiatric disorders: insomnia, disorientation, confusional state, and depression (includes depressed mood, depression, suicidal ideation, and completed suicide)

Respiratory, thoracic and mediastinal disorders: dyspnea (includes acute respiratory failure, dyspnea, dyspnea exertional, respiratory failure, respiratory distress, bronchospasm, bronchial hyperreactivity, tachypnea, and wheezing), cough, and productive cough

Vascular disorders: hypotension (includes blood pressure decreased, hypotension, hypovolemic shock, and circulatory collapse), hypertension (includes blood pressure increased, hypertension, and hypertensive crisis), flushing (includes flushing and hot flush), and capillary leak syndrome

B-cell Precursor ALL in the Consolidation Phase

Study E1910

The safety of a consolidation regimen comprised of multiple cycles of BLINCYTO monotherapy in addition to multiple cycles of chemotherapy (BLINCYTO arm) was evaluated in a randomized trial in adult patients with newly diagnosed Philadelphia chromosome-negative B-cell precursor ALL (Study E1910) [NCT02003222] [see Clinical Studies (14.3)] which included 111 patients treated in the BLINCYTO arm and 112 patients treated in the chemotherapy alone arm. In the BLINCYTO arm, the median (range) of cycles was 8 (1-8) (4 cycles of BLINCYTO and 4 cycles of chemotherapy). In the chemotherapy alone arm, the median (range) of cycles was 4 (1-4).

Fatal adverse reactions occurred in 2 patients (2%) during BLINCYTO cycles and were due to infection (n = 1) and coagulopathy (n = 1). Permanent discontinuation of BLINCYTO due to an adverse reaction occurred in 2% of patients. Dosage interruptions of BLINCYTO due to an adverse reaction occurred in 5% of patients. Dose reductions of BLINCYTO due to an adverse reaction occurred in 28% of patients.

The most common (≥ 20%) adverse reactions during consolidation cycles in the BLINCYTO arm were neutropenia, thrombocytopenia, anemia, leukopenia, headache, infection, nausea, lymphopenia, diarrhea, musculoskeletal pain, and tremor. The adverse reactions occurring at a difference between arms in incidence of ≥ 10% for All Grades or ≥ 5% for Grade 3 or higher are summarized in Table 9.

Table 9. Adverse Reactions with a Difference Between Arms of ≥ 10% for Any Grade or ≥ 5% for Grade 3 or 4 during Consolidation (Study E1910)
 | Consolidation Consisting of
Adverse Reaction | BLINCYTO Cycles + Chemotherapy Cycles (n = 111) |  | Chemotherapy Cycles Alone (n = 112)
Adverse Reaction | All Grades (%) [Includes the following fatal adverse reaction: infection (n = 1).] | Grade 3 or 4 (%) | All Grades (%) | Grade 3 or 4 (%)
Blood and lymphatic system disorders
Neutropenia [Other related adverse reactions included:] | 82 | 77 | 89 | 89
Thrombocytopenia | 75 | 57 | 75 | 71
Anemia | 59 | 29 | 50 | 38
Leukopenia | 43 | 41 | 57 | 56
Lymphopenia | 32 | 30 | 25 | 23
Febrile neutropenia | 19 | 19 | 25 | 25
Gastrointestinal disorders
Nausea [Nausea: vomiting;] | 32 | 5 | 22 | 4
Diarrhea | 29 | 3 | 15 | 3
Immune system disorders
Cytokine release syndrome [Cytokine release syndrome: capillary leak syndrome;] | 16 | 4 | 0 | 0
Infections and infestations
Infection – pathogen unspecified | 35 | 31 | 22 | 21
Musculoskeletal and connective tissue disorders
Musculoskeletal pain [Musculoskeletal pain: pain in extremity, back pain, arthralgia, myalgia, neck pain, flank pain, bone pain, non-cardiac chest pain;] | 23 | 5 | 5 | 4
Nervous system disorders
Headache [May represent ICANS.] | 41 | 5 | 30 | 5
Tremor | 23 | 3 | 3 | 0
Aphasia [Aphasia: dysarthria.] , | 10 | 8 | 0 | 0
Vascular disorders
Hypertension | 12 | 10 | 5 | 3

Study 20120215

The safety of BLINCYTO as the 3rd cycle of the consolidation phase was evaluated in a randomized, open-label study (Study 20120215) following induction and two cycles of consolidation chemotherapy in pediatric and young adult patients with high-risk first-relapsed B-cell precursor ALL [see Clinical Studies (14.3)]. The study included 54 patients treated with one cycle of BLINCYTO and 52 patients treated with one cycle of chemotherapy.

Serious adverse reactions occurred in 28% of patients who received BLINCYTO. Permanent discontinuation of BLINCYTO due to an adverse reaction occurred in 4% of patients. Adverse reactions that led to discontinuation included nervous system disorder and seizure. Dosage interruptions of BLINCYTO due to an adverse reaction occurred in 11% of patients. Adverse reactions which required dosage interruption in > 2% of patients included nervous system disorder.

The most common (≥ 20%) adverse reactions in the BLINCYTO arm were pyrexia, nausea, headache, rash, hypogammaglobulinemia, and anemia. The adverse reactions occurring at a difference of ≥ 10% incidence for any grade or at a difference of ≥ 5% incidence for Grade 3 or 4 between the BLINCYTO arm and chemotherapy arm are summarized in Table 10.

Table 10. Adverse Reactions with a Difference Between Arms of ≥ 10% for Any Grade or ≥ 5% for Grade 3 or 4 during Consolidation Cycle 3 (Study 20120215)
Adverse Reaction | BLINCYTO (n = 54) |  | Chemotherapy (n = 52)
Adverse Reaction | All Grades (%) | Grade 3 or 4 (%) | All Grades (%) | Grade 3 or 4 (%)
Blood and lymphatic system disorders
Anemia [Other related adverse reactions included:] | 24 | 15 | 46 | 42
Neutropenia | 19 | 17 | 35 | 31
Thrombocytopenia | 15 | 15 | 39 | 35
Febrile neutropenia | 2 | 2 | 25 | 25
Gastrointestinal disorders
Nausea [Nausea: vomiting;] | 43 | 2 | 31 | 2
Abdominal pain | 13 | 0 | 23 | 2
Stomatitis [Stomatitis: mouth ulceration, mucosal inflammation;] | 11 | 4 | 60 | 29
General disorders and administration site conditions
Pyrexia | 76 | 6 | 19 | 0
Hepatobiliary disorders
Liver function test abnormal [Liver function test abnormal: alanine aminotransferase increased, aspartate aminotransferase increased, gamma-glutamyltransferase increased, hypertransaminasemia;] | 9 | 6 | 27 | 17
Immune system disorders
Hypogammaglobulinemia | 24 | 2 | 12 | 2
Infections and infestations
Infection – pathogen unspecified | 13 | 6 | 29 | 10
Musculoskeletal and connective tissue disorders
Musculoskeletal pain [Musculoskeletal pain: back pain, pain in extremity, bone pain;] | 9 | 0 | 29 | 2
Nervous system disorders
Headache [May represent ICANS.] | 37 | 0 | 15 | 0
Skin and subcutaneous disorders
Rash | 22 | 2 | 12 | 0
Vascular disorders
Hemorrhage [Hemorrhage: Epistaxis, petechiae, hemarthrosis, hematoma, hematuria.] | 11 | 2 | 23 | 6

6.2 Postmarketing Experience

The following adverse reactions have been identified during postapproval use of BLINCYTO. Because these reactions are reported voluntarily from a population of uncertain size, it is not always possible to reliably estimate their frequency or establish a causal relationship to drug exposure.

- Fatal pancreatitis in patients receiving BLINCYTO in combination with dexamethasone.

7 DRUG INTERACTIONS

No formal drug interaction studies have been conducted with BLINCYTO. Initiation of BLINCYTO treatment causes transient release of cytokines that may suppress CYP450 enzymes. The highest drug-drug interaction risk is during the first 9 days of the first cycle and the first 2 days of the second cycle in patients who are receiving concomitant CYP450 substrates, particularly those with a narrow therapeutic index. In these patients, monitor for toxicity (e.g., warfarin) or drug concentrations (e.g., cyclosporine). Adjust the dose of the concomitant drug as needed [see Clinical Pharmacology (12.2, 12.3)].

8 USE IN SPECIFIC POPULATIONS

8.1 Pregnancy

Risk Summary

Based on its mechanism of action, BLINCYTO may cause fetal harm when administered to a pregnant woman [see Clinical Pharmacology (12.1)]. There are no available data on the use of BLINCYTO in pregnant women to evaluate for a drug-associated risk. In animal reproduction studies, a murine surrogate molecule administered to pregnant mice crossed the placental barrier (see Data).

Blinatumomab causes T-cell activation and cytokine release; immune activation may compromise pregnancy maintenance. In addition, based on expression of CD19 on B-cells and the finding of B-cell depletion in non-pregnant animals, blinatumomab can cause B-cell lymphocytopenia in infants exposed to blinatumomab in-utero. Advise pregnant women of the potential risk to a fetus.

In the U.S. general population, the estimated background risk of major birth defects and miscarriage in clinically recognized pregnancies is 2-4% and 15-20%, respectively.

Clinical Considerations

Fetal/Neonatal Adverse Reactions

Due to the potential for B-cell lymphocytopenia in infants following exposure to BLINCYTO in utero, the infant's B lymphocytes should be monitored before the initiation of live virus vaccination [see Warnings and Precautions (5.11)].

Data

Animal Data

Animal reproduction studies have not been conducted with blinatumomab. In embryo-fetal developmental toxicity studies, a murine surrogate molecule was administered intravenously to pregnant mice during the period of organogenesis. The surrogate molecule crossed the placental barrier and did not cause embryo-fetal toxicity or teratogenicity. The expected depletions of B and T cells were observed in the pregnant mice, but hematological effects were not assessed in fetuses.

8.2 Lactation

Risk Summary

There is no information regarding the presence of blinatumomab in human milk, the effects on the breastfed infant, or the effects on milk production. Because many drugs are excreted in human milk and because of the potential for serious adverse reactions in breastfed infants from BLINCYTO, including B-cell lymphocytopenia, advise patients not to breastfeed during treatment with BLINCYTO and for 48 hours after the last dose.

8.3 Females and Males of Reproductive Potential

BLINCYTO may cause fetal harm when administered to a pregnant woman [see Use in Specific Populations (8.1)].

Pregnancy Testing

Verify the pregnancy status of females of reproductive potential prior to initiating BLINCYTO treatment.

Contraception

Females

Advise females of reproductive potential to use effective contraception during treatment with BLINCYTO and for 48 hours after the last dose.

8.4 Pediatric Use

The safety and efficacy of BLINCYTO in pediatric patients less than 1 month of age have not been established for any indication [see Indications and Usage (1)].

Minimal Residual Disease (MRD)-Positive B-cell Precursor ALL

The safety and efficacy of BLINCYTO for the treatment of CD19-positive B-cell precursor acute lymphoblastic leukemia (ALL) in first or second complete remission with minimal residual disease (MRD) greater than or equal to 0.1% have been established in pediatric patients one month and older. Use of BLINCYTO is supported by evidence from two randomized, controlled trials (Study AALL1331, NCT02101853 and Study 20120215, NCT02393859) [see Clinical Studies (14.3)] in pediatric patients with first relapsed B-cell precursor ALL. Both studies included pediatric patients with MRD-positive B-cell precursor ALL. The studies included pediatric patients treated with BLINCYTO in the following age groups: 6 infants (1 month up to less than 2 years), 165 children (2 years up to less than 12 years), and 70 adolescents (12 years to less than 17 years). In general, the adverse reactions in BLINCYTO-treated pediatric patients were similar in type to those seen in adult patients with MRD-positive ALL [see Adverse Reactions (6.1)], and no differences in safety were observed between the different pediatric age subgroups.

Relapsed or Refractory B-cell Precursor ALL

The safety and efficacy of BLINCYTO have been established in pediatric patients one month and older with relapsed or refractory B-cell precursor ALL. Use of BLINCYTO is supported by a single-arm trial in pediatric patients with relapsed or refractory B-cell precursor ALL. This study included pediatric patients in the following age groups: 10 infants (1 month up to less than 2 years), 40 children (2 years up to less than 12 years), and 20 adolescents (12 years to less than 18 years). No differences in efficacy were observed between the different age subgroups [see Clinical Studies (14.2)].

In general, the adverse reactions in BLINCYTO-treated pediatric patients with relapsed or refractory ALL were similar in type to those seen in adult patients with relapsed or refractory B-cell precursor ALL [see Adverse Reactions (6.1)]. Adverse reactions that were observed more frequently (≥ 10% difference) in the pediatric population compared to the adult population were pyrexia (80% vs. 61%), hypertension (26% vs. 8%), anemia (41% vs. 24%), infusion-related reaction (49% vs. 34%), thrombocytopenia (34% vs. 21%), leukopenia (24% vs. 11%), and weight increased (17% vs. 6%).

In pediatric patients less than 2 years old (infants) with relapsed or refractory ALL, the incidence of neurologic toxicities was not significantly different than for the other age groups, but its manifestations were different; the only event terms reported were agitation, headache, insomnia, somnolence, and irritability. Infants also had an increased incidence of hypokalemia (50%) compared to other pediatric age cohorts (15-20%) or adults (17%).

B-cell Precursor ALL in the Consolidation Phase

The safety and efficacy of BLINCYTO for the treatment of Philadelphia-chromosome negative B-cell precursor ALL in the consolidation phase have been established in pediatric patients one month and older. Use of BLINCYTO for this indication is supported by extrapolation from a randomized controlled study in adults (Study E1910, NCT02003222) and evidence from two randomized, controlled studies in pediatric patients (Study 20120215 and Study AALL1331) [see Adverse Reactions (6.1), Use in Specific Populations (8.4), Clinical Pharmacology (12.3), and Clinical Studies (14.3)].

Benzyl Alcohol Toxicity in Neonates

Serious and fatal adverse reactions, including "gasping syndrome," can occur in very low birth weight (VLBW) neonates born weighing less than 1500 g, and early preterm neonates (infants born less than 34 weeks gestational age) treated with benzyl alcohol-preserved drugs intravenously. The "gasping syndrome" is characterized by central nervous system depression, metabolic acidosis, and gasping respirations. In these cases, benzyl alcohol dosages of 99 to 234 mg/kg/day produced high concentrations of benzyl alcohol and its metabolite in the blood and urine (blood concentration of benzyl alcohol were 0.61 to 1.378 mmol/L). Additional adverse reactions included gradual neurological deterioration, seizures, intracranial hemorrhage, hematologic abnormalities, skin breakdown, hepatic and renal failure, hypotension, bradycardia, and cardiovascular collapse. The minimum amount of benzyl alcohol at which serious adverse reactions may occur in neonates is not known [see Warnings and Precautions (5.12)].

Use the preservative-free formulations of BLINCYTO where possible in neonates. When prescribing BLINCYTO (with preservative) in neonatal patients, consider the combined daily metabolic load of benzyl alcohol from all sources including BLINCYTO (with preservative). The BLINCYTO 72-Hour bag (with preservative) and 96-Hour bag (with preservative) contain 2.5 mg of benzyl alcohol per mL, and the 7-Day bag (with preservative) contains 7.4 mg of benzyl alcohol per mL. The administration of BLINCYTO as a 72-hour, 96-hour, and 7-day infusion is not recommended for patients weighing less than 5.4 kg [see Warnings and Precautions (5.12)].

Benzyl alcohol administration may contribute to metabolic acidosis in pediatric patients, particularly those with immaturity of the metabolic pathway for alcohol, or those with underlying conditions or receiving concomitant medications that could predispose to acid base imbalance. Monitor these patients during use of BLINCYTO (with preservative) for new or worsening metabolic acidosis.

8.5 Geriatric Use

There were 158 (7%) patients 65 years and older in clinical studies of BLINCYTO for patients with MRD positive, CD19-positive B-cell precursor ALL in first or second complete remission, relapsed or refractory CD19-positive B-cell precursor ALL, and CD19-positive, Philadelphia-chromosome negative B-cell precursor ALL in the consolidation phase. Of the total number of BLINCYTO-treated patients in these studies, 123 (8%) were 65 years of age and older and 21 (1%) were 75 years of age or older. No overall differences in safety or effectiveness were observed between these patients and younger patients, and other reported clinical experience has not identified differences in responses between the elderly and younger patients. However, elderly patients experienced a higher rate of serious infections and neurological toxicities, including cognitive disorder, encephalopathy, and confusion [see Warnings and Precautions (5.2, 5.3)].

10 OVERDOSAGE

Overdoses have been observed, including one adult patient who received 133-fold the recommended therapeutic dose of BLINCYTO delivered over a short duration.

In the dose evaluation phase of a study in pediatric and adolescent patients with relapsed or refractory B-cell precursor ALL, one patient experienced a fatal cardiac failure event in the setting of life-threatening cytokine release syndrome (CRS) at a 30 mcg/m^2/day (higher than the maximum tolerated/recommended) dose [see Warnings and Precautions (5.1) and Adverse Reactions (6)].

Overdoses resulted in adverse reactions, which were consistent with the reactions observed at the recommended dosage and included fever, tremors, and headache. In the event of overdose, interrupt the infusion, monitor the patient for signs of adverse reactions, and provide supportive care [see Warnings and Precautions (5.10)]. Consider re-initiation of BLINCYTO at the recommended dosage when all adverse reactions have resolved and no earlier than 12 hours after interruption of the infusion [see Dosage and Administration (2.1, 2.2 and 2.3)].

11 DESCRIPTION

Blinatumomab is a bispecific CD19-directed CD3 T-cell engager. Blinatumomab is produced in Chinese hamster ovary cells. It consists of 504 amino acids and has a molecular weight of approximately 54 kilodaltons.

Each BLINCYTO package contains one vial BLINCYTO and one vial IV Solution Stabilizer.

BLINCYTO (blinatumomab) for injection is supplied in a single-dose vial as a sterile, preservative-free, white to off-white lyophilized powder for intravenous use. Each single-dose vial of BLINCYTO contains 35 mcg blinatumomab, citric acid monohydrate (3.35 mg), lysine hydrochloride (23.23 mg), polysorbate 80 (0.64 mg), trehalose dihydrate (95.5 mg), and sodium hydroxide to adjust pH to 7.0. After reconstitution with 3 mL of preservative-free Sterile Water for Injection, USP, the resulting concentration is 12.5 mcg/mL blinatumomab.

IV Solution Stabilizer is supplied in a single-dose vial as a sterile, preservative-free, colorless to slightly yellow, clear solution. Each single-dose vial of IV Solution Stabilizer contains citric acid monohydrate (52.5 mg), lysine hydrochloride (2283.8 mg), polysorbate 80 (10 mg), sodium hydroxide to adjust pH to 7.0, and water for injection.

12 CLINICAL PHARMACOLOGY

12.1 Mechanism of Action

Blinatumomab is a bispecific CD19-directed CD3 T-cell engager that binds to CD19 expressed on the surface of cells of B-lineage origin and CD3 expressed on the surface of T-cells. It activates endogenous T-cells by connecting CD3 in the T-cell receptor (TCR) complex with CD19 on benign and malignant B-cells. Blinatumomab mediates the formation of a synapse between the T-cell and the tumor cell, upregulation of cell adhesion molecules, production of cytolytic proteins, release of inflammatory cytokines, and proliferation of T-cells, which result in redirected lysis of CD19+ cells.

12.2 Pharmacodynamics

During the continuous intravenous infusion over 4 weeks, the pharmacodynamic response was characterized by T-cell activation and initial redistribution, reduction in peripheral B-cells, and transient cytokine elevation.

Peripheral T-cell redistribution (i.e., T-cell adhesion to blood vessel endothelium and/or transmigration into tissue) occurred after start of BLINCYTO infusion or dose escalation. T-cell counts initially declined within 1 to 2 days and then returned to baseline levels within 7 to 14 days in the majority of patients. Increase of T-cell counts above baseline (T-cell expansion) was observed in few patients.

Peripheral B-cell counts decreased to less than or equal to 10 cells/microliter during the first treatment cycle at doses ≥ 5 mcg/m^2/day or ≥ 9 mcg/day in the majority of patients. No recovery of peripheral B-cell counts was observed during the 2-week BLINCYTO-free period between treatment cycles. Incomplete depletion of B-cells occurred at doses of 0.5 mcg/m^2/day and 1.5 mcg/m^2/day and in a few patients at higher doses.

Cytokines including IL-2, IL-4, IL-6, IL-8, IL-10, IL-12, TNF-α, and IFN-γ were measured, and IL-6, IL-10, and IFN-γ were elevated. The highest elevation of cytokines was observed in the first 2 days following start of BLINCYTO infusion. The elevated cytokine levels returned to baseline within 24 to 48 hours during the infusion. In subsequent treatment cycles, cytokine elevation occurred in fewer patients with lesser intensity compared to the initial 48 hours of the first treatment cycle.

12.3 Pharmacokinetics

The pharmacokinetics of blinatumomab appear linear over a dose range from 5 to 90 mcg/m^2/day (approximately equivalent to 9 to 162 mcg/day) in adult patients. Following continuous intravenous infusion, the steady-state serum concentration (Css) was achieved within a day and remained stable over time. The increase in mean Css values was approximately proportional to the dose in the range tested. At the clinical doses of 9 mcg/day and 28 mcg/day for the treatment of relapsed or refractory ALL, the mean (SD) Css was 228 (356) pg/mL and 616 (537) pg/mL, respectively. The pharmacokinetics of blinatumomab in adult patients with MRD-positive B-cell precursor ALL and in adult patients with B-cell precursor ALL in the consolidation phase were similar to adult patients with relapsed or refractory ALL.

Distribution

The estimated mean (SD) volume of distribution based on terminal phase (Vz) was 5.27 (4.37) L with continuous intravenous infusion of blinatumomab.

Elimination

The estimated mean (SD) systemic clearance with continuous intravenous infusion in patients receiving blinatumomab in clinical studies was 3.10 (2.94) L/hour. The mean (SD) half-life was 2.20 (1.34) hours. Negligible amounts of blinatumomab were excreted in the urine at the tested clinical doses.

Metabolism

The metabolic pathway of blinatumomab has not been characterized. Like other protein therapeutics, blinatumomab is expected to be degraded into small peptides and amino acids via catabolic pathways.

Specific Populations

There were no clinically meaningful differences in the pharmacokinetics of blinatumomab based on age (0.6 to 80 years of age), sex, race (72% White, 17% Asian, 3% Black), ethnicity, Philadelphia chromosome status or mild (total bilirubin ≤ upper limit of normal [ULN] and AST > ULN or total bilirubin > 1 to 1.5 × ULN and any AST) or moderate hepatic impairment (total bilirubin > 1.5 to 3 × ULN and any AST). The effect of other races or severe hepatic impairment (total bilirubin > 3 × ULN, any AST) on the pharmacokinetics of blinatumomab is unknown. Body surface area (0.4 to 2.9 m^2) influences the pharmacokinetics of blinatumomab, supporting BSA-based dosing in patients < 45 kg.

Pediatric Patients

The pharmacokinetics of blinatumomab appear linear over a dose range from 5 to 30 mcg/m^2/day in pediatric patients. At the recommended doses of 5 and 15 mcg/m^2/day for the treatment of relapsed or refractory B-cell precursor ALL, the mean (SD) steady-state concentration (Css) values were 162 (179) and 533 (392) pg/mL, respectively. The pharmacokinetics of blinatumomab in pediatric patients with MRD-positive B-cell precursor ALL and in pediatric patients with B-cell precursor ALL in the consolidation phase were similar to pediatric patients with relapsed or refractory ALL.

In all pediatric patients with ALL, the estimated mean (SD) volume of distribution (Vz), clearance (CL), and terminal half-life (t1/2,z) in Cycle 1 were 4.14 (3.32) L/m^2, 1.65 (1.62) L/hour/m^2, and 2.14 (1.44) hours, respectively.

The steady-state concentrations of blinatumomab were comparable in adult and pediatric patients at the equivalent dose levels based on BSA-based regimens.

Patients with Renal Impairment

Pharmacokinetic analyses showed an approximately 2-fold difference in mean blinatumomab clearance values between patients with moderate renal impairment (CrCL ranging from 30 to 59 mL/min, N = 49) and normal renal function (CrCL more than 90 mL/min, N = 674). However, high interpatient variability was discerned (CV% up to 98.4%), and clearance values in renal impaired patients were essentially within the range observed in patients with normal renal function. There is no information available in patients with severe renal impairment (CrCL 15-29 mL/min) or patients on hemodialysis.

Drug Interaction Studies

Transient elevation of cytokines may suppress CYP450 enzyme activities [see Drug Interactions (7) and Clinical Pharmacology (12.2)].

12.6 Immunogenicity

The observed incidence of anti-drug antibody is highly dependent on the sensitivity and specificity of the assay. Differences in assay methods preclude meaningful comparisons of the incidence of anti-drug antibody in the studies described below with the incidence of anti-drug antibodies in other studies, including those of BLINCYTO.

The immunogenicity of BLINCYTO has been evaluated using either an electrochemiluminescence detection technology (ECL) or an enzyme-linked immunosorbent assay (ELISA) screening immunoassay for the detection of binding anti-blinatumomab antibodies. For patients whose sera tested positive in the screening immunoassay, an in vitro biological assay was performed to detect neutralizing antibodies.

In clinical studies, less than 2% of patients treated with BLINCYTO tested positive for binding anti-blinatumomab antibodies. Of patients who developed anti-blinatumomab antibodies, 7 out of 9 (78%) had in vitro neutralizing activity. Anti-blinatumomab antibody formation may affect pharmacokinetics of BLINCYTO.

Overall, the totality of clinical evidence supports the finding that anti-blinatumomab antibodies are not suggestive of any clinical impact on the safety or effectiveness of BLINCYTO.

13 NONCLINICAL TOXICOLOGY

13.1 Carcinogenesis, Mutagenesis, Impairment of Fertility

No carcinogenicity or genotoxicity studies have been conducted with blinatumomab.

No studies have been conducted to evaluate the effects of blinatumomab on fertility. A murine surrogate molecule had no adverse effects on male and female reproductive organs in a 13-week repeat-dose toxicity study in mice.

14 CLINICAL STUDIES

14.1 MRD-positive B-cell Precursor ALL

BLAST Study

The efficacy of BLINCYTO was evaluated in an open-label, multicenter, single-arm study (BLAST Study) [NCT01207388] that included patients who were ≥ 18 years of age, had received at least 3 chemotherapy blocks of standard ALL therapy, were in hematologic complete remission (defined as < 5% blasts in bone marrow, absolute neutrophil count > 1 Gi/L, platelets > 100 Gi/L) and had MRD at a level of ≥ 0.1% using an assay with a minimum sensitivity of 0.01%. BLINCYTO was administered at a constant dose of 15 mcg/m^2/day (equivalent to the recommended dosage of 28 mcg/day) intravenously for all treatment cycles. Patients received up to 4 cycles of treatment. Dose adjustment was possible in case of adverse events.

The treated population included 86 patients in first or second hematologic complete remission (CR1 or CR2). The demographics and baseline characteristics are shown in Table 11. The median number of treatment cycles was 2 (range: 1 to 4). Following treatment with BLINCYTO, 45 out of 61 (73.8%) patients in CR1 and 14 out of 25 (56.0%) patients in CR2 underwent allogeneic hematopoietic stem cell transplantation in continuous hematologic complete remission.

Table 11. Demographics and Baseline Characteristics in BLAST Study
Characteristics | BLINCYTO (N = 86)
Age
Median, years (min, max) | 43 (18, 76)
≥ 65 years, n (%) | 10 (12)
Males, n (%) | 50 (58)
Race, n (%)
Asian | 1 (1)
Other (mixed) | 0 (0)
White | 76 (88)
Unknown | 9 (11)
Philadelphia chromosome disease status, n (%)
Positive | 1 (1)
Negative | 85 (99)
Relapse history, n (%)
Patients in 1st CR | 61 (71)
Patients in 2nd CR | 25 (29)
MRD level at baseline [Assessed centrally using an assay with minimum sensitivity of 0.01%.] , n (%)
≥ 10% | 7 (8)
≥ 1% and < 10% | 34 (40)
≥ 0.1% and < 1% | 45 (52)

Efficacy was based on achievement of undetectable MRD within one cycle of BLINCYTO treatment and hematological relapse-free survival (RFS). The assay used to assess MRD response had a sensitivity of 0.01% for 6 patients and ≤ 0.005% for 80 patients. Overall, undetectable MRD was achieved by 70 patients (81.4%: 95% CI: 71.6%, 89.0%). The median hematological RFS was 22.3 months. Table 12 shows the MRD response and hematological RFS by remission number.

Table 12. Efficacy Results in Patients ≥ 18 Years of Age with MRD-positive B-cell Precursor ALL (BLAST Study)
 | Patients in CR1 (n = 61) | Patients in CR2 (n = 25)
Complete MRD response [Complete MRD response was defined as the absence of detectable MRD confirmed in an assay with minimum sensitivity of 0.01%.] , n (%), [95% CI] | 52 (85.2) [73.8, 93.0] | 18 (72.0) [50.6, 87.9]
Median hematological relapse-free survival [Relapse was defined as either hematological or extramedullary relapse, secondary leukemia, or death due to any cause; Includes time after transplantation; Kaplan-Meier estimate.] in months (range) | 35.2 (0.4, 53.5) | 12.3 (0.7, 42.3)

Undetectable MRD was achieved by 65 of 80 patients (81.3%: 95% CI: 71.0%, 89.1%) with an assay sensitivity of at least 0.005%. The estimated median hematological RFS among the 80 patients using the higher sensitivity assay was 24.2 months (95% CI: 17.9, NE).

14.2 Relapsed/Refractory B-cell Precursor ALL

TOWER Study

The efficacy of BLINCYTO was compared to standard of care (SOC) chemotherapy in a randomized, open-label, multicenter study (TOWER Study) [NCT02013167]. Eligible patients were ≥ 18 years of age with relapsed or refractory B-cell precursor ALL [> 5% blasts in the bone marrow and refractory to primary induction therapy or refractory to last therapy, untreated first relapse with first remission duration < 12 months, untreated second or later relapse, or relapse at any time after allogeneic hematopoietic stem cell transplantation (alloHSCT)]. BLINCYTO was administered at 9 mcg/day on Days 1-7 and 28 mcg/day on Days 8-28 for Cycle 1, and 28 mcg/day on Days 1-28 for Cycles 2-5 in 42-day cycles and for Cycles 6-9 in 84-day cycles. Dose adjustment was possible in case of adverse events. SOC chemotherapy included fludarabine, cytarabine arabinoside, and granulocyte colony-stimulating factor (FLAG); high-dose cytarabine arabinoside (HiDAC); high-dose methotrexate- (HDMTX) based combination; or clofarabine/clofarabine-based regimens.

There were 405 patients randomized 2:1 to receive BLINCYTO or investigator-selected SOC chemotherapy. Randomization was stratified by age (< 35 years vs. ≥ 35 years of age), prior salvage therapy (yes vs. no), and prior alloHSCT (yes vs. no) as assessed at the time of consent. The demographics and baseline characteristics were well-balanced between the two arms (see Table 13).

Table 13. Demographics and Baseline Characteristics in TOWER Study
Characteristics | BLINCYTO (N = 271) | Standard of Care (SOC) Chemotherapy (N = 134)
Age
Median, years (min, max) | 37 (18, 80) | 37 (18, 78)
< 35 years, n (%) | 124 (46) | 60 (45)
≥ 35 years, n (%) | 147 (54) | 74 (55)
≥ 65 years, n (%) | 33 (12) | 15 (11)
≥ 75 years, n (%) | 10 (4) | 2 (2)
Males, n (%) | 162 (60) | 77 (58)
Race, n (%)
American Indian or Alaska Native | 4 (2) | 1 (1)
Asian | 19 (7) | 9 (7)
Black (or African American) | 5 (2) | 3 (2)
Multiple | 2 (1) | 0
Native Hawaiian or Other Pacific Islander | 1 (0) | 1 (1)
Other | 12 (4) | 8 (6)
White | 228 (84) | 112 (84)
Prior salvage therapy | 171 (63) | 70 (52)
Prior alloHSCT [alloHSCT = allogeneic hematopoietic stem cell transplantation.] | 94 (35) | 46 (34)
Eastern Cooperative Group Status - n (%)
0 | 96 (35) | 52 (39)
1 | 134 (49) | 61 (46)
2 | 41 (15) | 20 (15)
Unknown | 0 | 1 (1)
Refractory to salvage treatment - n (%)
Yes | 87 (32) | 34 (25)
No | 182 (67) | 99 (74)
Unknown | 2 (1) | 1 (1)
Maximum of central/local bone marrow blasts - n (%)
≤ 5% | 0 | 0
> 5 to < 10% | 9 (3) | 7 (5)
10 to < 50% | 60 (22) | 23 (17)
≥ 50% | 201 (74) | 104 (78)
Unknown | 1 (0) | 0

Of the 271 patients randomized to the BLINCYTO arm, 267 patients received BLINCYTO treatment. The median number of treatment cycles was two (range: 1 to 9 cycles); 267 (99%) received Cycles 1-2 (induction), 86 (32%) received Cycles 3-5 (consolidation), and 27 (10%) received Cycles 6-9 (continued therapy). Of the 134 patients on the SOC arm, 25 dropped out prior to start of study treatment, and 109 patients received a median of 1 treatment cycle (range: 1 to 4 cycles).

The determination of efficacy was based on overall survival (OS). The study demonstrated statistically significant improvement in OS for patients treated with BLINCYTO as compared to SOC chemotherapy.

See Figure 1 and Table 14 below for efficacy results from the TOWER Study.

Figure 1. Kaplan-Meier Curve of Overall Survival in TOWER Study

Table 14. Efficacy Results in Patients ≥ 18 Years of Age with Philadelphia Chromosome-Negative Relapsed or Refractory B-cell Precursor ALL (TOWER Study)
 | BLINCYTO (N = 271) | SOC Chemotherapy (N = 134)
Overall Survival
Number of deaths (%) | 164 (61) | 87 (65)
Median, months [95% CI] | 7.7 [5.6, 9.6] | 4.0 [2.9, 5.3]
Hazard Ratio [95% CI] [Based on stratified Cox's model.] | 0.71 [0.55, 0.93]
p-value [The p-value was derived using stratified log rank test.] | 0.012
Overall Response
CR [CR (complete remission) was defined as ≤ 5% blasts in the bone marrow, no evidence of disease, and full recovery of peripheral blood counts (platelets > 100,000/microliter and absolute neutrophil counts [ANC] > 1,000/microliter).] /CRh* [CRh* (complete remission with partial hematologic recovery) was defined as ≤ 5% blasts in the bone marrow, no evidence of disease, and partial recovery of peripheral blood counts (platelets > 50,000/microliter and ANC > 500/microliter).] , n (%) [95% CI] | 115 (42) [37, 49] | 27 (20) [14, 28]
Treatment difference [95% CI] | 22 [13, 31]
p-value [The p-value was derived using Cochran-Mantel-Haenszel test.] | < 0.001
CR, n (%) [95% CI] | 91 (34) [28, 40] | 21 (16) [10, 23]
Treatment difference [95% CI] | 18 [10, 26]
p-value | < 0.001
MRD Response [MRD (minimum residual disease) response was defined as MRD by PCR or flow cytometry < 1 × 10^-4 (0.01%).] for CR/CRh*
n1/n2 (%) [n1: number of patients who achieved MRD response and CR/CRh*; n2: number of patients who achieved CR/CRh* and had a postbaseline assessment.] [95% CI] | 73/115 (64) [54, 72] | 14/27 (52) [32, 71]

Study MT103-211

Study MT103-211 [NCT01466179] was an open-label, multicenter, single-arm study. Eligible patients were ≥ 18 years of age with Philadelphia chromosome-negative relapsed or refractory B-cell precursor ALL (relapsed with first remission duration of ≤ 12 months in first salvage or relapsed or refractory after first salvage therapy or relapsed within 12 months of alloHSCT, and had ≥ 10% blasts in bone marrow).

BLINCYTO was administered as a continuous intravenous infusion. The recommended dose for this study was determined to be 9 mcg/day on Days 1-7 and 28 mcg/day on Days 8-28 for Cycle 1, and 28 mcg/day on Days 1-28 for subsequent cycles. Dose adjustment was possible in case of adverse events. The treated population included 185 patients who received at least 1 infusion of BLINCYTO; the median number of treatment cycles was 2 (range: 1 to 5). Patients who responded to BLINCYTO but later relapsed had the option to be retreated with BLINCYTO. Among treated patients, the median age was 39 years (range: 18 to 79 years), 63 out of 185 (34.1%) had undergone HSCT prior to receiving BLINCYTO, and 32 out of 185 (17.3%) had received more than 2 prior salvage therapies.

Efficacy was based on the complete remission (CR) rate, duration of CR, and proportion of patients with an MRD-negative CR/CR with partial hematological recovery (CR/CRh*) within 2 cycles of treatment with BLINCYTO. Table 15 shows the efficacy results from this study. The HSCT rate among those who achieved CR/CRh* was 39% (30 out of 77).

Table 15. Efficacy Results in Patients ≥ 18 Years of Age with Philadelphia Chromosome-Negative Relapsed or Refractory B-cell Precursor ALL (Study MT103-211)
 | N = 185
 | CR [CR (complete remission) was defined as ≤ 5% of blasts in the bone marrow, no evidence of disease, and full recovery of peripheral blood counts (platelets > 100,000/microliter and absolute neutrophil counts [ANC] > 1,000/microliter).] | CRh* [CRh* (complete remission with partial hematological recovery) was defined as ≤ 5% of blasts in the bone marrow, no evidence of disease, and partial recovery of peripheral blood counts (platelets > 50,000/microliter and ANC > 500/microliter).] | CR/CRh*
n (%) [95% CI] | 60 (32.4) [25.7, 39.7] | 17 (9.2) [5.4, 14.3] | 77 (41.6) [34.4, 49.1]
MRD response [MRD (minimal residual disease) response was defined as MRD by PCR < 1 × 10^-4 (0.01%).]
n1/n2 (%) [n1: number of patients who achieved MRD response and the respective remission status; n2: number of patients who achieved the respective remission status. Six CR/CRh* responders with missing MRD data were considered as MRD-nonresponders.] [95% CI] | 48/60 (80.0) [67.7, 89.2] | 10/17 (58.8) [32.9, 81.6] | 58/77 (75.3) [64.2, 84.4]
DOR/RFS [DOR (duration of response)/RFS (relapse-free survival) was defined as time since first response of CR or CRh* to relapse or death, whichever is earlier. Relapse was defined as hematological relapse (blasts in bone marrow greater than 5% following CR) or an extramedullary relapse.]
Median (months) (range) | 6.7 (0.46 – 16.5) | 5.0 (0.13 – 8.8) | 5.9 (0.13 – 16.5)

ALCANTARA Study

The efficacy of BLINCYTO for treatment of Philadelphia chromosome-positive B-cell precursor ALL was evaluated in an open-label, multicenter, single-arm study (ALCANTARA Study) [NCT02000427]. Eligible patients were ≥ 18 years of age with Philadelphia chromosome-positive B-cell precursor ALL, relapsed or refractory to at least 1 second generation or later tyrosine kinase inhibitor (TKI), or intolerant to second generation TKI, and intolerant or refractory to imatinib mesylate.

BLINCYTO was administered at 9 mcg/day on Days 1-7 and 28 mcg/day on Days 8-28 for Cycle 1, and 28 mcg/day on Days 1-28 for subsequent cycles. Dose adjustment was possible in case of adverse events.

The treated population included 45 patients who received at least one infusion of BLINCYTO; the median number of treatment cycles was 2 (range: 1 to 5). The demographics and baseline characteristics are shown in Table 16.

Table 16. Demographics and Baseline Characteristics in ALCANTARA Study
Characteristics | BLINCYTO (N = 45)
Age
Median, years (min, max) | 55 (23, 78)
≥ 65 years and < 75 years, n (%) | 10 (22)
≥ 75 years, n (%) | 2 (4)
Males, n (%) | 24 (53)
Race, n (%)
Asian | 1 (2)
Black (or African American) | 3 (7)
Other | 2 (4)
White | 39 (87)
Disease History
Prior TKI treatment [Number of patients that failed ponatinib = 23 (51%)] , n (%)
1 | 7 (16)
2 | 21 (47)
≥ 3 | 17 (38)
Prior salvage therapy | 31 (62)
Prior alloHSCT [alloHSCT = allogeneic hematopoietic stem cell transplantation] | 20 (44)
Bone marrow blasts [centrally assessed]
≥ 50% to < 75% | 6 (13)
≥ 75% | 28 (62)

Efficacy was based on the complete remission (CR) rate, duration of CR, and proportion of patients with an MRD-negative CR/CR with partial hematological recovery (CR/CRh*) within 2 cycles of treatment with BLINCYTO. Table 17 shows the efficacy results from ALCANTARA Study. Five of the 16 responding (31%) patients underwent allogeneic HSCT in CR/CRh* induced with BLINCYTO. There were 10 patients with documented T315I mutation; four achieved CR within 2 cycles of treatment with BLINCYTO.

Table 17. Efficacy Results in Patients ≥ 18 Years of Age with Philadelphia Chromosome-Positive Relapsed or Refractory B-cell Precursor ALL (ALCANTARA Study)
 | N = 45
 | CR [CR (complete remission) was defined as ≤ 5% of blasts in the bone marrow, no evidence of disease, and full recovery of peripheral blood counts (platelets > 100,000/microliter and absolute neutrophil counts [ANC] > 1,000/microliter).] | CRh* [CRh* (complete remission with partial hematological recovery) was defined as ≤ 5% of blasts in the bone marrow, no evidence of disease, and partial recovery of peripheral blood counts (platelets > 50,000/microliter and ANC > 500/microliter).] | CR/CRh*
n (%) [95% CI] | 14 (31) [18, 47] | 2 (4) [1, 15] | 16 (36) [22, 51]
MRD response [MRD (minimal residual disease) response was defined as MRD by PCR < 1 × 10^-4 (0.01%).]
n1/n2 (%) [n1: number of patients who achieved MRD response and the respective remission status; n2: number of patients who achieved the respective remission status. Six CR/CRh* responders with missing MRD data were considered as MRD-nonresponders.] [95% CI] | 12/14 (86) [57, 98] | 2/2 (100) [16, 100] | 14/16 (88) [62, 98]
DOR/RFS [DOR (duration of response)/RFS (relapse-free survival) was defined as time since first response of CR or CRh* to relapse or death, whichever is earlier. Relapse was defined as hematological relapse (blasts in bone marrow greater than 5% following CR) or an extramedullary relapse.]
Median (months) (range) | 6.7 (3.6 – 12.0) | NE [NE = not estimable] (3.7 – 9.0) | 6.7 (3.6 – 12.0)

Study MT103-205

Study MT103-205 [NCT01471782] was an open-label, multicenter, single-arm study in pediatric patients with relapsed or refractory B-cell precursor ALL (second or later bone marrow relapse, any marrow relapse after allogeneic HSCT, or refractory to other treatments, and had > 25% blasts in bone marrow). BLINCYTO was administered at 5 mcg/m^2/day on Days 1-7 and 15 mcg/m^2/day on Days 8-28 for Cycle 1, and 15 mcg/m^2/day on Days 1-28 for subsequent cycles. Dose adjustment was possible in case of adverse events. Patients who responded to BLINCYTO but later relapsed had the option to be retreated with BLINCYTO.

Among the 70 treated patients, the median age was 8 years (range: 7 months to 17 years), 40 out of 70 (57.1%) had undergone allogeneic HSCT prior to receiving BLINCYTO, and 39 out of 70 (55.7%) had refractory disease. The median number of treatment cycles was 1 (range: 1 to 5).

Twenty-three out of 70 (32.9%) patients achieved CR/CRh* within the first 2 treatment cycles with 17 out of 23 (73.9%) occurring within Cycle 1 of treatment. See Table 18 for the efficacy results from the study. The HSCT rate among those who achieved CR/CRh* was 48% (11 out of 23).

Table 18. Efficacy Results in Patients < 18 Years of Age with Relapsed or Refractory B-cell Precursor ALL (Study MT103-205)
 | N = 70
 | CR [CR (complete remission) was defined as ≤ 5% of blasts in the bone marrow, no evidence of circulating blasts or extra-medullary disease, and full recovery of peripheral blood counts (platelets > 100,000/microliter and absolute neutrophil counts [ANC] > 1,000/microliter).] | CRh* [CRh* (complete remission with partial hematological recovery) was defined as ≤ 5% of blasts in the bone marrow, no evidence of circulating blasts or extramedullary disease, and partial recovery of peripheral blood counts (platelets > 50,000/microliter and ANC > 500/microliter).] | CR/CRh*
n (%) [95% CI] | 12 (17.1) [9.2, 28.0] | 11 (15.7) [8.1, 26.4] | 23 (32.9) [22.1, 45.1]
MRD response [MRD (minimal residual disease) response was defined as MRD by PCR or flow cytometry < 1 × 10^-4 (0.01%).]
n1/n2 (%) [n1: number of patients who achieved MRD response and the respective remission status; n2: number of patients who achieved the respective remission status. One CR/CRh* responder with missing MRD data was considered as a MRD-nonresponder.] [95% CI] | 6/12 (50.0) [21.1, 78.9] | 4/11 (36.4) [10.9, 69.2] | 10/23 (43.5) [23.2, 65.5]
DOR/RFS [DOR (duration of response)/RFS (relapse-free survival) was defined as time since first response of CR or CRh* to relapse or death, whichever is earlier. Relapse was defined as hematological relapse (blasts in bone marrow greater than 5% following CR) or an extramedullary relapse.]
Median (months) (range) | 6.0 (0.5 – 12.1) | 3.5 (0.5 – 16.4) | 6.0 (0.5 – 16.4)

14.3 Philadelphia Chromosome-Negative B-cell Precursor ALL in the Consolidation Phase

Study E1910

The efficacy of BLINCYTO was evaluated in a randomized, controlled study in adult patients with newly diagnosed Philadelphia chromosome-negative B-cell precursor ALL (Study E1910) [NCT02003222]. Eligible patients in hematologic complete remission (CR) or CR with incomplete peripheral blood count recovery (CRi) following induction and intensification chemotherapy were randomized 1:1 to receive a consolidation regimen comprised of multiple cycles of BLINCYTO monotherapy in addition to multiple cycles of intensive chemotherapy (BLINCYTO arm) or to intensive chemotherapy alone (chemotherapy arm). Randomization was stratified by age (< 55 years versus ≥ 55 years), CD20 status, rituximab use, and intent to undergo allogeneic stem cell transplantation (HSCT).

The postremission treatment consisted of a BFM-like chemotherapy regimen adapted from the E2993/UKALLXII clinical trial. Patients randomized to the BLINCYTO arm were to receive 2 cycles of BLINCYTO followed by 3 cycles of consolidation chemotherapy, then a third cycle of BLINCYTO followed by the fourth cycle of chemotherapy and a fourth cycle of BLINCYTO (total 8 cycles). BLINCYTO was administered as a continuous intravenous infusion at 28 mcg/day on Days 1-28. Patients randomized to the chemotherapy arm of the study were to receive 4 cycles of chemotherapy alone (total 4 cycles). Patients on the BLINCYTO arm could go to HSCT after 1 - 2 cycles of BLINCYTO and up to 2 cycles of consolidation chemotherapy, and patients randomized to the chemotherapy arm could go to HSCT after intensification and up to 3 cycles of consolidation chemotherapy. All patients who completed consolidation but did not go to HSCT received maintenance therapy through 2 1/2 years from the start of intensification.

The demographics and baseline characteristics are provided in Table 19.

Table 19. Demographics and Baseline Characteristics in Study E1910
Characteristics | Consolidation Consisting of
Characteristics | BLINCYTO Cycles + Chemotherapy Cycles (n = 112) | Chemotherapy Cycles Alone (n = 112)
Age
Median, years (min, max) | 52 (31, 69) | 50 (30, 70)
Males, n (%) | 55 (49) | 56 (50)
Race, n (%)
American Indian or Alaska Native | 2 (2) | 1 (1)
Asian | 3 (3) | 2 (2)
Black (or African American) | 9 (8) | 4 (4)
Native Hawaiian or Other Pacific Islander | 1 (1) | 0
White | 87 (78) | 89 (79)
Not Reported | 5 (4) | 6 (5)
Unknown | 5 (4) | 10 (9)
Ethnicity, n (%)
Hispanic or Latino | 13 (12) | 10 (9)
Not Hispanic or Latino | 95 (85) | 95 (85)
Not Reported | 1 (1) | 2 (2)
Unknown | 3 (3) | 5 (4)
Stratification Factors, n (%)
Age < 55 years at randomization | 65 (58) | 65 (58)
CD20 positive | 45 (40) | 46 (41)
Rituximab use | 33 (29) | 36 (32)
Planned allogeneic SCT [allogeneic SCT = allogeneic stem cell transplantation.] | 36 (32) | 35 (31)

Efficacy was established on the basis of overall survival (OS). The results with a median follow-up of 3.6 years are shown in Figure 2 and Table 20.

Figure 2. Kaplan-Meier for Overall Survival in Study E1910

KM = Kaplan-Meier. CI = Confidence Interval. N = Number of patients in the analysis set.
Censor indicated by vertical bar.

Table 20. Overall Survival in Study E1910
 | BLINCYTO + Chemotherapy | Chemotherapy
Number of patients | 112 | 112
Overall Survival
3-year Kaplan-Meier estimate (%) [95% CI] | 84.8 [76.3, 90.4] | 69.0 [58.7, 77.2]
Hazard ratio [95% CI] [The hazard ratio estimates are obtained from a stratified Cox regression model at the 3rd interim analysis.] | 0.42 [0.24, 0.75]
p-value [The p-value was derived using the stratified log rank test.] | 0.003
CI = Confidence interval. Overall survival (OS) is calculated from time of randomization until death due to any cause.

In a later analysis with a median follow-up of 4.5 years, the 5-year OS was 82.4% [95% CI (73.7, 88.4)] in the BLINCYTO + chemotherapy arm and 62.5% [95% CI (52.0, 71.3)] in the chemotherapy arm. The hazard ratio was 0.44 [95% CI (0.25, 0.76)].

Study 20120215

The efficacy of BLINCYTO compared to consolidation chemotherapy was evaluated in a randomized, controlled, open-label, multicenter study (Study 20120215) [NCT02393859]. Eligible patients were 28 days to 18 years old and had high-risk, first-relapsed, Philadelphia chromosome-negative B-cell precursor ALL with < 25% blasts in the bone marrow after induction and 2 cycles of consolidation chemotherapy. Patients were randomized 1:1 to receive BLINCYTO or the IntReALLHR2010 HC3 intensive combination chemotherapy as the third cycle of consolidation. Patients in the BLINCYTO arm received one cycle of BLINCYTO as a continuous intravenous infusion at 15 mcg/m^2/day over 4 weeks (maximum daily dose was not to exceed 28 mcg/day). Randomization was stratified by age, minimal residual disease status determined at the end of induction based on local assessment, and bone marrow status determined at the end of the second block of consolidation chemotherapy. Patients were to proceed to HSCT after this cycle of consolidation.

There were 54 patients randomized to the BLINCYTO arm and 57 to the chemotherapy arm. The demographics and baseline characteristics are shown in Table 21.

Table 21. Demographics and Baseline Characteristics in Study 20120215
Characteristics | Consolidation Cycle 3
Characteristics | BLINCYTO (N = 54) | Chemotherapy (N = 57)
Age, n (%)
Median, (range) | 6 (1, 17) | 5 (1, 17)
< 1 year | 0 | 0
1 to 9 years | 39 (72) | 41 (72)
≥ 10 to 18 years | 15 (28) | 16 (28)
Males, n (%) | 30 (56) | 23 (40)
Race, n (%)
American Indian or Alaska Native | 0 | 0
Asian | 1 (2) | 3 (5)
Black (or African American) | 0 | 3 (5)
Native Hawaiian or Other Pacific Islander | 0 | 0
Other | 3 (6) | 5 (9)
White | 50 (93) | 46 (81)
Cytomorphology at randomization, n (%)
Blasts < 5% | 54 (100) | 54 (95)
Blasts ≥ 5% and < 25% | 0 | 2 (4)
Blasts ≥ 25% blasts | 0 | 0
Not evaluable | 0 | 1 (2)
MRD PCR value at randomization, n (%)
≥ 10^-3 | 11 (20) | 16 (28)
< 10^-3 and ≥ 10^-4 | 15 (28) | 6 (11)
< 10^-4 | 20 (37) | 23 (40)
Unknown | 8 (15) | 12 (21)
Time from first diagnosis to relapse (month), n (%)
< 18 months | 19 (35) | 22 (39)
≥ 18 months and ≤ 30 months | 32 (59) | 31 (54)
> 30 months | 3 (6) | 4 (7)
N = number of patients in the analysis set; n = number of patients with observed data; MRD = minimal residual disease; PCR = polymerase chain reaction.

Efficacy was established on the basis of overall survival (OS) and relapse-free survival (RFS). See Table 22, Figure 3, and Figure 4 for results of OS and RFS from Study 20120215.

Table 22. Efficacy Results in Pediatric Patients with High-Risk First Relapsed B-cell Precursor ALL (Study 20120215)
 | Consolidation Cycle 3
 | BLINCYTO (N = 54) | Chemotherapy (N = 57)
Overall Survival
Number of deaths (%) | 11 (20.4) | 28 (49.1)
5-year KM estimate (%) [95% CI] [Months were calculated as days from randomization date to event/censor date, divided by 30.5.] | 78.4 [64.2, 87.4] | 41.4 [26.3, 55.9]
Hazard Ratio [95% CI] [The hazard ratio estimates are obtained from the Cox proportional hazard model.] | 0.35 [0.17, 0.70]
Relapse-free Survival
Events, n (%) | 20 (37.0) | 37 (64.9)
5-year KM estimate (%) [95% CI] | 61.1 [46.3, 72.9] | 27.6 [16.2, 40.3]
Hazard Ratio [95% CI] | 0.38 [0.22, 0.66]
NE = Not estimable. CI = Confidence interval.

The median follow-up time for OS was 55.2 months for the overall population. Figure 3 presents a Kaplan-Meier plot comparing OS between treatment arms for the overall population.

Figure 3. Kaplan-Meier for Overall Survival (Study 20120215)

KM = Kaplan-Meier. CI = Confidence Interval. N = Number of patients in the analysis set.
Censor indicated by vertical bar.

Figure 4. Kaplan-Meier for Relapse-free Survival (Study 20120215)

KM = Kaplan-Meier. CI = Confidence Interval. N = Number of patients in the analysis set.
Censor indicated by vertical bar.

16 HOW SUPPLIED/STORAGE AND HANDLING

Each BLINCYTO package (NDC 55513-160-01) contains:

- One BLINCYTO (blinatumomab) for injection 35 mcg single-dose vial containing a sterile, preservative-free, white to off-white lyophilized powder and
- One IV Solution Stabilizer 10 mL single-dose glass vial containing a sterile, preservative-free, colorless to slightly yellow, clear solution.

STORAGE AND HANDLING

Store BLINCYTO and IV Solution Stabilizer vials in the original package refrigerated at 2°C to 8°C (36°F to 46°F) and protect from light until time of use. Do not freeze.

BLINCYTO and IV Solution Stabilizer vials may be stored for a maximum of 8 hours at room temperature [23°C to 27°C (73°F to 81°F)] in the original carton to protect from light.

17 PATIENT COUNSELING INFORMATION

Advise the patient to read the FDA-approved patient labeling (Medication Guide).

Cytokine Release Syndrome (CRS)

Advise patients of the risk of CRS and infusion reactions, and to contact their healthcare professional for signs and symptoms associated with CRS or infusion reactions (pyrexia, fatigue, nausea, vomiting, chills, hypotension, rash, and wheezing) [see Warnings and Precautions (5.1) and Adverse Reactions (6.1)].

Neurological Toxicities, including Immune Effector Cell-Associated Neurotoxicity Syndrome

Advise patients of the risk of neurological toxicities, including ICANS, and to contact their healthcare professional for signs and symptoms associated with this event (including convulsions, speech disorders, and confusion) [see Warnings and Precautions (5.2) and Adverse Reactions (6.1)].

Infections

Advise patients of the risk of infections, and to contact their healthcare professional for signs or symptoms of infection [see Warnings and Precautions (5.3) and Adverse Reactions (6.1)].

Inform patients of the importance of keeping the skin clean around the intravenous catheter to reduce the risk of infection.

Pancreatitis

Advise patients of the risk of pancreatitis and to contact their healthcare provider for signs or symptoms of pancreatitis, which include severe and persistent stomach pain, with or without nausea and vomiting [see Warnings and Precautions (5.8) and Adverse Reactions (6.2)].

Driving and Engaging in Hazardous Occupations

Advise patients to refrain from driving and engaging in hazardous occupations or activities such as operating heavy or potentially dangerous machinery while BLINCYTO is being administered. Patients should be advised that they may experience neurological events, including seizures and ICANS [see Warnings and Precautions (5.6)].

Infusion Pump Errors

Inform patients they should not adjust the setting on the infusion pump. Any changes to pump function may result in dosing errors. If there is a problem with the infusion pump or the pump alarms, patients should contact their doctor or nurse immediately.

Embryo-Fetal Toxicity

Advise pregnant women of the potential risk to a fetus. Advise females of reproductive potential to inform their healthcare provider if they are pregnant or become pregnant [see Warnings and Precautions (5.13) and Use in Specific Populations (8.1)]. Advise females of reproductive potential to use effective contraception during treatment with BLINCYTO and for 48 hours after the last dose [see Warnings and Precautions (5.13) and Use in Specific Populations (8.3)].

Lactation

Advise women not to breastfeed during treatment with BLINCYTO and for 48 hours after the last dose [see Use in Specific Populations (8.2)].

BLINCYTO® (blinatumomab)

Manufactured by:
Amgen Inc.
One Amgen Center Drive
Thousand Oaks, California 91320-1799
U.S. License No. 1080

Patent: http://pat.amgen.com/blincyto/

© 2014-2025 Amgen Inc. All rights reserved.
V20

Medication Guide
BLINCYTO® (blin sye toe)
(blinatumomab)
for injection

What is the most important information I should know about BLINCYTO?
Call your healthcare provider or get emergency medical help right away if you get any of the symptoms listed below.
BLINCYTO may cause serious side effects that can be severe, life-threatening, or lead to death, including:

- Cytokine Release Syndrome (CRS) and Infusion Reactions. Symptoms of CRS and infusion reactions may include:

- fever
- tiredness or weakness
- dizziness
- headache
- low blood pressure
- nausea

- vomiting
- chills
- face swelling
- wheezing or trouble breathing
- skin rash

- Neurologic problems. Symptoms of neurologic problems may include:

- seizures
- difficulty in speaking or slurred speech
- loss of consciousness
- trouble sleeping
- confusion and disorientation

- loss of balance
- headache
- difficulty with facial movements, hearing, vision, or swallowing
- tremors

People with Down Syndrome may have a higher risk of seizures with BLINCYTO treatment and may be given anti-seizure medicine before starting BLINCYTO treatment.

Your healthcare provider will check for these problems during treatment with BLINCYTO. Your healthcare provider may temporarily stop or completely stop your treatment with BLINCYTO, if you have severe side effects.
See “What are the possible side effects of BLINCYTO?” below for other side effects of BLINCYTO.

What is BLINCYTO?
BLINCYTO is a prescription medicine used to treat adults and children 1 month and older with:

- B-cell precursor acute lymphoblastic leukemia (ALL) in remission when only a small number of cancer cells remain in the body (minimal residual disease)
- B-cell precursor ALL that has come back or did not respond to previous treatments
- Philadelphia-chromosome negative B-cell precursor ALL in the consolidation phase of chemotherapy treatment with multiple phases

ALL is a cancer of the blood in which a particular kind of white blood cell is growing out of control.
It is not known if BLINCYTO is safe and effective in children less than 1 month of age.

Who should not receive BLINCYTO?
Do not receive BLINCYTO if you are allergic to blinatumomab or to any of the ingredients of BLINCYTO. See the end of this Medication Guide for a complete list of ingredients in BLINCYTO.

Before receiving BLINCYTO, tell your healthcare provider about all of your medical conditions, including if you or your child:

- have a history of neurological problems, such as seizures, confusion, trouble speaking or loss of balance
- have Down Syndrome
- have an infection
- have ever had an infusion reaction after receiving BLINCYTO or other medications
- have a history of radiation treatment to the brain, or chemotherapy treatment
- are scheduled to receive a vaccine. You should not receive a “live vaccine” for at least 2 weeks before you start treatment with BLINCYTO, during treatment, and until your immune system recovers after you receive your last cycle of BLINCYTO. If you are not sure about the type of vaccine, ask your healthcare provider.
- are pregnant or plan to become pregnant. BLINCYTO may harm your unborn baby. Tell your healthcare provider if you become pregnant during treatment with BLINCYTO.
  - If you are able to become pregnant, your healthcare provider should do a pregnancy test before you start treatment with BLINCYTO.
  - Females who are able to become pregnant should use an effective form of birth control (contraception) during treatment with BLINCYTO, and for 48 hours after your last dose of BLINCYTO.
- are breastfeeding or plan to breastfeed. It is not known if BLINCYTO passes into your breast milk. You should not breastfeed during treatment with BLINCYTO and for 48 hours after your last dose.

Tell your healthcare provider about all the medicines you take, including prescription and over-the-counter medicines, vitamins, and herbal supplements.

How will I receive BLINCYTO?

- BLINCYTO will be given to you by intravenous (IV) infusion into your vein by an infusion pump.
- Your healthcare provider will decide the number of treatment cycles of BLINCYTO.
  - You will receive BLINCYTO by continuous IV infusion for 4 weeks (28 days), followed by a 2-week (14 days) break during which you will not receive BLINCYTO. This is 1 treatment cycle (42 days).
- Your healthcare provider may prescribe continued therapy.
  - You will receive BLINCYTO by continuous IV infusion for 4 weeks (28 days), followed by an 8-week (56 days) break during which you will not receive BLINCYTO. This is 1 treatment cycle (84 days).
- Your healthcare provider may give you BLINCYTO in a hospital or clinic for the first 3 or 9 days of the first treatment cycle and for the first 2 days of the second cycle to check you for side effects. If you receive additional treatment cycles of BLINCYTO or if your treatment is stopped for a period of time and restarted, you may also be treated in a hospital or clinic.
- Your healthcare provider may change your dose of BLINCYTO, delay, or completely stop treatment with BLINCYTO if you have certain side effects.
- Your healthcare provider will do blood tests during treatment with BLINCYTO to check you for side effects.
- Before you receive BLINCYTO, you will be given a corticosteroid medicine to help reduce infusion reactions.
- Before and during treatment with BLINCYTO, you may be given chemotherapy as an injection into the space that surrounds the spinal cord and the brain (intrathecal injection) to help prevent central nervous system relapse of ALL.
- It is very important to keep the area around the IV catheter clean to reduce the risk of getting an infection. Your healthcare provider will show you how to care for your catheter site.
- Do not change the settings on your infusion pump, even if there is a problem with your pump or your pump alarm sounds. Any changes to your infusion pump settings may cause a dose that is too high or too low to be given.

Call your healthcare provider or nurse right away if you have any problems with your pump or your pump alarm sounds.

What should I avoid while receiving BLINCYTO?
Do not drive, operate heavy machinery, or do other dangerous activities while you are receiving BLINCYTO because BLINCYTO can cause neurological symptoms, such as dizziness, seizures, and confusion.

What are the possible side effects of BLINCYTO?
BLINCYTO may cause serious side effects, including:
See “What is the most important information I should know about BLINCYTO?”

- Infections. BLINCYTO may cause life-threatening infections that may lead to death. Tell your healthcare provider right away if you develop any signs or symptoms of an infection.
- Tumor Lysis Syndrome (TLS). TLS is caused by the fast breakdown of cancer cells. TLS can be life-threatening and may lead to death. Tell your healthcare provider right away if you have any symptoms of TLS during treatment with BLINCYTO, including:

- nausea and vomiting
- confusion
- shortness of breath
- irregular heartbeat

- dark or cloudy urine
- reduced amount of urine
- unusual tiredness
- muscle cramps

- Low white blood cell counts (neutropenia). Neutropenia is common with BLINCYTO treatment and may sometimes be life-threatening. Low white blood cell counts can increase your risk of infection. Your healthcare provider will do blood tests to check your white blood cell count during treatment with BLINCYTO. Tell your healthcare provider right away if you get a fever.
- Abnormal liver blood tests. Your healthcare provider will do blood tests to check your liver before you start BLINCYTO and during treatment with BLINCYTO.
- Inflammation of the pancreas (pancreatitis). Pancreatitis may happen in people treated with BLINCYTO and corticosteroids. It may be severe and lead to death. Tell your healthcare provider right away if you have severe stomach-area pain that does not go away. The pain may happen with or without nausea and vomiting.

The most common side effects of BLINCYTO include:

- fever
- reactions related to infusion of the medicine such as face swelling, low blood pressure, and high blood pressure (infusion-related reactions)
- headache
- infection

- muscle, joint and bone pain
- low white blood cell count (neutropenia)
- nausea
- low red blood cell count (anemia)
- low platelet count (thrombocytopenia)
- diarrhea

These are not all the possible side effects of BLINCYTO.
Call your doctor for medical advice about side effects. You may report side effects to FDA at 1-800-FDA-1088.

How should I store BLINCYTO?
Intravenous (IV) bags containing BLINCYTO for infusion will arrive in a special package.

- Do not open the package.
- Do not freeze the package.
- The package containing BLINCYTO will be opened by your healthcare provider and stored in the refrigerator at 36°F to 46°F (2°C to 8°C).
- Do not throw away (dispose of) any BLINCYTO in your household trash. Talk with your healthcare provider about disposal of BLINCYTO and used supplies.

Keep BLINCYTO and all medicines out of reach of children.

General information about safe and effective use of BLINCYTO.
Medicines are sometimes prescribed for purposes other than those listed in a Medication Guide. Do not use BLINCYTO for a condition for which it was not prescribed. Do not give BLINCYTO to other people even if they have the same symptoms that you have. It may harm them. You can ask your pharmacist or healthcare provider for information about BLINCYTO that is written for health professionals.

What are the ingredients in BLINCYTO?
Active ingredient: blinatumomab
Inactive ingredients: citric acid monohydrate, lysine hydrochloride, polysorbate 80, trehalose dihydrate, sodium hydroxide and preservative-free sterile water for injection.
Inactive ingredients of IV Solution Stabilizer: citric acid monohydrate, lysine hydrochloride, polysorbate 80, sodium hydroxide and water for injection.
Manufactured by: Amgen Inc., One Amgen Center Drive, Thousand Oaks, CA 91320-1799
U.S. License No. 1080 © 2014-2025 Amgen Inc. All rights reserved. v13
For more information, go to www.blincyto.com or call Amgen at 1-800-772-6436.

This Medication Guide has been approved by the U.S. Food and Drug Administration.

Revised: 4/2025

24-Hour or 48-Hour Infusion
INSTRUCTIONS FOR USE: 24-HOUR OR 48-HOUR INFUSION
The preparation steps differ based on the infusion duration.
Follow the steps specific to the infusion duration you are preparing.
It is very important that the instructions for preparation (including admixing) and administration provided in this section are strictly followed to minimize medication errors (including underdose and overdose) [see Dosage and Administration (2.5), Warnings and Precautions (5.10)].
Aseptic Preparation
Strictly observe aseptic technique when preparing the solution for infusion since BLINCYTO vials do not contain antimicrobial preservatives. To prevent accidental contamination, prepare BLINCYTO according to aseptic standards, including but not limited to:
- Prepare BLINCYTO in a USP <797> compliant facility.
- Prepare BLINCYTO in an ISO Class 5 laminar flow hood or better.
- Ensure that the admixing area has appropriate environmental specifications, confirmed by periodic monitoring.
- Ensure that personnel are appropriately trained in aseptic manipulations and admixing of oncology drugs.
- Ensure that personnel wear appropriate protective clothing and gloves.
- Ensure that gloves and surfaces are disinfected.
Gather Equipment and Supplies for 24-Hour or 48-Hour Infusion
- Preservative-Free Sterile Water for Injection, USP.
- Preservative-Free 0.9% Sodium Chloride Injection, USP.
- Sterile, non-pyrogenic, low protein-binding, 0.2 micron in-line filter.
- Infusion bags/pump cassettes and intravenous tubing sets: Use either polyolefin, DEHP-free PVC, or ethyl vinyl acetate (EVA).
  - BLINCYTO is incompatible with diethylhexylphthalate (DEHP) due to the possibility of particle formation, leading to a cloudy solution.
- BLINCYTO package(s), each BLINCYTO package contains:
  - One BLINCYTO for injection 35 mcg single-dose vial containing a sterile, preservative-free, white to off-white lyophilized powder.
    - More than one vial of BLINCYTO may be needed to prepare the recommended dose.
  - One IV Solution Stabilizer 10 mL single-dose glass vial containing a sterile, preservative-free, colorless to slightly yellow, clear solution.
    - Do not use IV Solution Stabilizer for reconstitution of BLINCYTO.
    - IV Solution Stabilizer is used to coat the intravenous bag prior to addition of reconstituted BLINCYTO to prevent adhesion of BLINCYTO to intravenous bags and intravenous tubing.
Preparation of BLINCYTO: Reconstitution
1. Determine the number of BLINCYTO vials needed for a dose and infusion duration.
  - Refer to Table 1 (patients weighing 45 kg or more) or Table 2 (patients weighing less than 45 kg).
a. Reconstitute each BLINCYTO vial with 3 mL of preservative-free Sterile Water for Injection, USP by directing the water along the walls of the BLINCYTO vial and not directly on the lyophilized powder. The resulting concentration per BLINCYTO vial is 12.5 mcg/mL.
  - Do not reconstitute BLINCYTO vials with the IV Solution Stabilizer (IVSS).
3 mL of Preservative-Free Sterile Water for Injection, USP |  |  |  | Lyophilized BLINCYTO |  |  | Reconstituted BLINCYTO
 | Important: Do not reconstitute BLINCYTO vials with IV Solution Stabilizer (IVSS).
b. Gently swirl contents to avoid excess foaming.
  - Do not shake.
c. Visually inspect the reconstituted solution for particulate matter and discoloration during reconstitution and prior to preparing the intravenous bag. The resulting solution should be clear to slightly opalescent, colorless to slightly yellow.
  - Do not use if solution is cloudy or has precipitated.
Preparation of BLINCYTO: 24-Hour or 48-Hour Intravenous Bag
2. Aseptically add 270 mL of preservative-free 0.9% Sodium Chloride Injection, USP to the empty intravenous bag.
 |  | 270 mL of Preservative-Free 0.9% NaCl Injection, USP |  |  |  |  | Empty IV Bag Material, use either:; - Polyolefin, - DEHP-free PVC, or - EVA IV Bag
3. Aseptically transfer 5.5 mL of IV Solution Stabilizer (IVSS) to the intravenous bag containing preservative-free 0.9% Sodium Chloride Injection, USP.
  - Gently mix the contents of the bag to avoid foaming.
 |  | IV Solution Stabilizer |  | - For 24-hour infusion, transfer 5.5 mL IV Solution Stabilizer. - For 48-hour infusion, transfer 5.5 mL IV Solution Stabilizer. - Discard the vial containing the unused IV Solution Stabilizer.
4. Aseptically transfer the required volume of reconstituted BLINCYTO solution into the intravenous bag containing preservative-free 0.9% Sodium Chloride Injection, USP and IV Solution Stabilizer.
  - Gently mix the contents of the bag to avoid foaming.
 |  | Reconstituted BLINCYTO |  | - Refer to Table 1 for patients weighing 45 kg or more for the specific volume of reconstituted BLINCYTO. - Refer to Table 2 for patients weighing less than 45 kg (dose based on BSA) for the specific volume of reconstituted BLINCYTO. - Discard the vial containing unused BLINCYTO.
5. Remove air from the intravenous bag. This is particularly important for use with an ambulatory infusion pump.
6. Under aseptic conditions, attach the intravenous tubing to the intravenous bag with the sterile 0.2 micron in-line filter.
  - Ensure that the intravenous tubing is compatible with the infusion pump.
  - Use either polyolefin, DEHP-free PVC or EVA intravenous tubing sets.
7. Prime the intravenous tubing only with the solution in the bag containing the FINAL prepared BLINCYTO solution for infusion.
8. Store refrigerated at 2°C to 8°C (36°F to 46°F) if not used immediately [see Dosage and Administration (2.6)].
 | Table 1. For 24-Hour and 48-Hour Infusion: Patients Weighing 45 kg or More
 | Infusion Duration |  | Dose |  | Reconstituted BLINCYTO
 | Infusion Duration |  | Dose |  | Volume |  | Vials
 | 24 hours |  | 9 mcg/day |  | 0.83 mL |  | 1
 | 24 hours |  | 28 mcg/day |  | 2.6 mL |  | 1
 | 48 hours |  | 9 mcg/day |  | 1.7 mL |  | 1
 | 48 hours |  | 28 mcg/day |  | 5.2 mL |  | 2
 | Table 2. For 24-Hour and 48-Hour Infusion: Patients Weighing Less Than 45 kg
 | Infusion Duration | Dose |  | BSA (m^2) |  | Reconstituted BLINCYTO
 | Infusion Duration | Dose |  | BSA (m^2) |  | Volume |  | Vials
 | 24 hours | 5 mcg/m^2/day |  | 1.5 – 1.59 |  | 0.7 mL |  | 1
 | 24 hours | 5 mcg/m^2/day |  | 1.4 – 1.49 |  | 0.66 mL |  | 1
 | 24 hours | 5 mcg/m^2/day |  | 1.3 – 1.39 |  | 0.61 mL |  | 1
 | 24 hours | 5 mcg/m^2/day |  | 1.2 – 1.29 |  | 0.56 mL |  | 1
 | 24 hours | 5 mcg/m^2/day |  | 1.1 – 1.19 |  | 0.52 mL |  | 1
 | 24 hours | 5 mcg/m^2/day |  | 1 – 1.09 |  | 0.47 mL |  | 1
 | 24 hours | 5 mcg/m^2/day |  | 0.9 – 0.99 |  | 0.43 mL |  | 1
 | 24 hours | 5 mcg/m^2/day |  | 0.8 – 0.89 |  | 0.38 mL |  | 1
 | 24 hours | 5 mcg/m^2/day |  | 0.7 – 0.79 |  | 0.33 mL |  | 1
 | 24 hours | 5 mcg/m^2/day |  | 0.6 – 0.69 |  | 0.29 mL |  | 1
 | 24 hours | 5 mcg/m^2/day |  | 0.5 – 0.59 |  | 0.24 mL |  | 1
 | 24 hours | 5 mcg/m^2/day |  | 0.4 – 0.49 |  | 0.2 mL |  | 1
 | 24 hours | 5 mcg/m^2/day |  | 0.35 – 0.39 |  | 0.17 mL |  | 1
 | 24 hours | 5 mcg/m^2/day |  | 0.3 – 0.34 |  | 0.15 mL |  | 1
 | 24 hours | 5 mcg/m^2/day |  | 0.25 – 0.29 |  | 0.12 mL |  | 1
 | 24 hours | 5 mcg/m^2/day |  | 0.2 – 0.24 |  | 0.1 mL |  | 1
 | 24 hours | 15 mcg/m^2/day |  | 1.5 – 1.59 |  | 2.1 mL |  | 1
 | 24 hours | 15 mcg/m^2/day |  | 1.4 – 1.49 |  | 2 mL |  | 1
 | 24 hours | 15 mcg/m^2/day |  | 1.3 – 1.39 |  | 1.8 mL |  | 1
 | 24 hours | 15 mcg/m^2/day |  | 1.2 – 1.29 |  | 1.7 mL |  | 1
 | 24 hours | 15 mcg/m^2/day |  | 1.1 – 1.19 |  | 1.6 mL |  | 1
 | 24 hours | 15 mcg/m^2/day |  | 1 – 1.09 |  | 1.4 mL |  | 1
 | 24 hours | 15 mcg/m^2/day |  | 0.9 – 0.99 |  | 1.3 mL |  | 1
 | 24 hours | 15 mcg/m^2/day |  | 0.8 – 0.89 |  | 1.1 mL |  | 1
 | 24 hours | 15 mcg/m^2/day |  | 0.7 – 0.79 |  | 1 mL |  | 1
 | 24 hours | 15 mcg/m^2/day |  | 0.6 – 0.69 |  | 0.86 mL |  | 1
 | 24 hours | 15 mcg/m^2/day |  | 0.5 – 0.59 |  | 0.72 mL |  | 1
 | 24 hours | 15 mcg/m^2/day |  | 0.4 – 0.49 |  | 0.59 mL |  | 1
 | 24 hours | 15 mcg/m^2/day |  | 0.35 – 0.39 |  | 0.51 mL |  | 1
 | 24 hours | 15 mcg/m^2/day |  | 0.3 – 0.34 |  | 0.44 mL |  | 1
 | 24 hours | 15 mcg/m^2/day |  | 0.25 – 0.29 |  | 0.37 mL |  | 1
 | 24 hours | 15 mcg/m^2/day |  | 0.2 – 0.24 |  | 0.3 mL |  | 1
 | 48 hours | 5 mcg/m^2/day |  | 1.5 – 1.59 |  | 1.4 mL |  | 1
 | 48 hours | 5 mcg/m^2/day |  | 1.4 – 1.49 |  | 1.3 mL |  | 1
 | 48 hours | 5 mcg/m^2/day |  | 1.3 – 1.39 |  | 1.2 mL |  | 1
 | 48 hours | 5 mcg/m^2/day |  | 1.2 – 1.29 |  | 1.1 mL |  | 1
 | 48 hours | 5 mcg/m^2/day |  | 1.1 – 1.19 |  | 1 mL |  | 1
 | 48 hours | 5 mcg/m^2/day |  | 1 – 1.09 |  | 0.94 mL |  | 1
 | 48 hours | 5 mcg/m^2/day |  | 0.9 – 0.99 |  | 0.85 mL |  | 1
 | 48 hours | 5 mcg/m^2/day |  | 0.8 – 0.89 |  | 0.76 mL |  | 1
 | 48 hours | 5 mcg/m^2/day |  | 0.7 – 0.79 |  | 0.67 mL |  | 1
 | 48 hours | 5 mcg/m^2/day |  | 0.6 – 0.69 |  | 0.57 mL |  | 1
 | 48 hours | 5 mcg/m^2/day |  | 0.5 – 0.59 |  | 0.48 mL |  | 1
 | 48 hours | 5 mcg/m^2/day |  | 0.4 – 0.49 |  | 0.39 mL |  | 1
 | 48 hours | 5 mcg/m^2/day |  | 0.35 – 0.39 |  | 0.34 mL |  | 1
 | 48 hours | 5 mcg/m^2/day |  | 0.3 – 0.34 |  | 0.29 mL |  | 1
 | 48 hours | 5 mcg/m^2/day |  | 0.25 – 0.29 |  | 0.25 mL |  | 1
 | 48 hours | 5 mcg/m^2/day |  | 0.2 – 0.24 |  | 0.2 mL |  | 1
 | 48 hours | 15 mcg/m^2/day |  | 1.5 – 1.59 |  | 4.2 mL |  | 2
 | 48 hours | 15 mcg/m^2/day |  | 1.4 – 1.49 |  | 3.9 mL |  | 2
 | 48 hours | 15 mcg/m^2/day |  | 1.3 – 1.39 |  | 3.7 mL |  | 2
 | 48 hours | 15 mcg/m^2/day |  | 1.2 – 1.29 |  | 3.4 mL |  | 2
 | 48 hours | 15 mcg/m^2/day |  | 1.1 – 1.19 |  | 3.1 mL |  | 2
 | 48 hours | 15 mcg/m^2/day |  | 1 – 1.09 |  | 2.8 mL |  | 1
 | 48 hours | 15 mcg/m^2/day |  | 0.9 – 0.99 |  | 2.6 mL |  | 1
 | 48 hours | 15 mcg/m^2/day |  | 0.8 – 0.89 |  | 2.3 mL |  | 1
 | 48 hours | 15 mcg/m^2/day |  | 0.7 – 0.79 |  | 2 mL |  | 1
 | 48 hours | 15 mcg/m^2/day |  | 0.6 – 0.69 |  | 1.7 mL |  | 1
 | 48 hours | 15 mcg/m^2/day |  | 0.5 – 0.59 |  | 1.4 mL |  | 1
 | 48 hours | 15 mcg/m^2/day |  | 0.4 – 0.49 |  | 1.2 mL |  | 1
 | 48 hours | 15 mcg/m^2/day |  | 0.35 – 0.39 |  | 1 mL |  | 1
 | 48 hours | 15 mcg/m^2/day |  | 0.3 – 0.34 |  | 0.88 mL |  | 1
 | 48 hours | 15 mcg/m^2/day |  | 0.25 – 0.29 |  | 0.75 mL |  | 1
 | 48 hours | 15 mcg/m^2/day |  | 0.2 – 0.24 |  | 0.61 mL |  | 1
Administration of BLINCYTO: 24-Hour or 48-Hour Intravenous Bag
- Administer BLINCYTO as a continuous intravenous infusion at a constant flow rate using an infusion pump. The pump should be programmable, lockable, non-elastomeric, and have an alarm.
- The starting volume (270 mL) is more than the volume administered to the patient (240 mL) to account for the priming of the intravenous tubing and to ensure that the patient will receive the full dose of BLINCYTO.
- Ensure that the intravenous tubing is primed only with the solution in the bag containing the FINAL prepared BLINCYTO solution for infusion.
- Administer the FINAL prepared BLINCYTO infusion solution using intravenous tubing that contains a sterile, non-pyrogenic, low protein-binding, 0.2 micron in-line filter for 24-hour or 48-hour bags.
  - For 72-hour, 96-hour, or 7-day bag administration information [see "Administration of BLINCYTO: 72-Hour, 96-Hour, or 7-Day Intravenous Bag"].
- Infuse the FINAL prepared BLINCYTO infusion solution according to the instructions on the pharmacy label on the prepared bag at one of the following constant infusion rates:
  - Infusion rate of 10 mL/hour for a duration of 24 hours, OR
  - Infusion rate of 5 mL/hour for a duration of 48 hours.
- Important Note: Do not flush the BLINCYTO infusion line, especially when changing infusion bags. Flushing when changing bags or at completion of infusion can result in excess dosage and complications thereof. When administering via a multi-lumen venous catheter, infuse BLINCYTO through a dedicated lumen. Before flushing the catheter system, residual amounts of BLINCYTO must be aspirated from the catheter system to avoid bolus administration.
- At the end of the infusion, any remaining solution in the intravenous bag and intravenous tubing should be discarded in accordance with local requirements.

72-Hour, 96-Hour, or 7-Day Infusion (Preservative)

INSTRUCTIONS FOR USE: 72-HOUR OR 96-HOUR, OR 7-DAY INFUSION
The preparation steps differ based on the infusion duration.
Follow the steps specific to the infusion duration you are preparing.
It is very important that the instructions for preparation (including admixing) and administration provided in this section are strictly followed to minimize medication errors (including underdose and overdose) [see Dosage and Administration (2.5), Warnings and Precautions (5.10)].
The administration of BLINCYTO as a 72-hour, 96-hour, and 7-day infusion is not recommended for patients weighing less than 5.4 kg [see Warnings and Precautions (5.12)].

Aseptic Preparation
Strictly observe aseptic technique when preparing the solution for infusion since BLINCYTO vials do not contain antimicrobial preservatives. To prevent accidental contamination, prepare BLINCYTO according to aseptic standards, including but not limited to:

- Prepare BLINCYTO in a USP <797> compliant facility.
- Prepare BLINCYTO in an ISO Class 5 laminar flow hood or better.
- Ensure that the admixing area has appropriate environmental specifications, confirmed by periodic monitoring.
- Ensure that personnel are appropriately trained in aseptic manipulations and admixing of oncology drugs.
- Ensure that personnel wear appropriate protective clothing and gloves.
- Ensure that gloves and surfaces are disinfected.

Gather Equipment and Supplies for 72-Hour, 96-Hour, or 7-Day Infusion

- Preservative-Free Sterile Water for Injection, USP.
- Preservative-Free 0.9% Sodium Chloride Injection, USP.
- Bacteriostatic 0.9% Sodium Chloride Injection, USP.
- Infusion bags/pump cassettes and intravenous tubing sets: Use either polyolefin, DEHP-free PVC, or ethyl vinyl acetate (EVA).
  - BLINCYTO is incompatible with diethylhexylphthalate (DEHP) due to the possibility of particle formation, leading to a cloudy solution.
- BLINCYTO package(s), each BLINCYTO package contains:
  - One BLINCYTO for injection 35 mcg single-dose vial containing a sterile, preservative-free, white to off-white lyophilized powder.
    - More than one vial of BLINCYTO may be needed to prepare the recommended dose.
  - One IV Solution Stabilizer 10 mL single-dose glass vial containing a sterile, preservative-free, colorless to slightly yellow, clear solution.
    - Do not use IV Solution Stabilizer for reconstitution of BLINCYTO.
    - IV Solution Stabilizer is used to coat the intravenous bag prior to addition of reconstituted BLINCYTO to prevent adhesion of BLINCYTO to intravenous bags and intravenous tubing.

Preparation of BLINCYTO: Reconstitution
1. Determine the number of BLINCYTO vials needed for a dose and infusion duration.
  - Refer to Table 3 (patients weighing 45 kg or more) or Table 4 (patients weighing between 5.4 kg and less than 45 kg).
a. Reconstitute each BLINCYTO vial with 3 mL of preservative-free Sterile Water for Injection, USP by directing the water along the walls of the BLINCYTO vial and not directly on the lyophilized powder. The resulting concentration per BLINCYTO vial is 12.5 mcg/mL.
  - Do not reconstitute BLINCYTO vials with the IV Solution Stabilizer (IVSS).
3 mL of Preservative-Free Sterile Water for Injection, USP |  |  |  |  | Lyophilized BLINCYTO |  |  | Reconstituted BLINCYTO
 |  | Important: Do not reconstitute BLINCYTO vials with IV Solution Stabilizer (IVSS).
b. Gently swirl contents to avoid excess foaming.
  - Do not shake.
c. Visually inspect the reconstituted solution for particulate matter and discoloration during reconstitution and prior to preparing the intravenous bag. The resulting solution should be clear to slightly opalescent, colorless to slightly yellow.
  - Do not use if solution is cloudy or has precipitated.
Preparation of BLINCYTO: 72-Hour, 96-Hour, or 7-Day Intravenous Bag
2. Aseptically add the required volume of Bacteriostatic 0.9% Sodium Chloride Injection, USP to the empty intravenous bag.
  - For 72-hour infusion, add 45 mL Bacteriostatic 0.9% Sodium Chloride Injection.
  - For 96-hour infusion, add 56 mL Bacteriostatic 0.9% Sodium Chloride Injection.
  - For 7-day infusion, add 90 mL Bacteriostatic 0.9% Sodium Chloride Injection.
 |  |  | Bacteriostatic 0.9% NaCl Injection, USP |  |  |  |  | Empty IV Bag Material, use either:; - Polyolefin, - DEHP-free PVC, or - EVA IV Bag
3. Aseptically transfer the required volume of IV Solution Stabilizer (IVSS) to the intravenous bag containing Bacteriostatic 0.9% Sodium Chloride Injection, USP.
  - Gently mix the contents of the bag to avoid foaming.
 |  |  | IV Solution Stabilizer | - For 72-hour infusion, transfer 3.2 mL IV Solution Stabilizer. - For 96-hour infusion, transfer 4 mL IV Solution Stabilizer. - For 7-day infusion, transfer 2.2 mL IV Solution Stabilizer. - Discard the vial containing the unused IV Solution Stabilizer.
4. Aseptically transfer the required volume of reconstituted BLINCYTO solution into the intravenous bag containing Bacteriostatic 0.9% Sodium Chloride Injection, USP and IV Solution Stabilizer.
  - Gently mix the contents of the bag to avoid foaming.
 |  |  | Reconstituted BLINCYTO | - Refer to Table 3 for patients weighing 45 kg or more for the specific volume of reconstituted BLINCYTO. - Refer to Table 4 for patients weighing between 5.4 kg and less than 45 kg (dose based on BSA) for the specific volume of reconstituted BLINCYTO. - Discard the vial containing unused BLINCYTO.
5. Aseptically add the needed volume of preservative-free 0.9% Sodium Chloride Injection, USP to the intravenous bag to obtain the final volumes within Table 3 and Table 4.
  - Gently mix the contents of the bag to avoid foaming.
 |  |  | Preservative-Free 0.9% NaCl Injection, USP | - Refer to Table 3 for patients weighing 45 kg or more for the specific volume of preservative-free 0.9% Sodium Chloride Injection, USP. - Refer to Table 4 for patients weighing between 5.4 kg and less than 45 kg (dose based on BSA) for the specific volume of preservative-free 0.9% Sodium Chloride Injection, USP.
6. Remove air from the intravenous bag. This is particularly important for use with an ambulatory infusion pump.
7. Under aseptic conditions, attach the intravenous tubing to the intravenous bag. Do not use an in-line filter for 72-hour, 96-hour, or 7-day bags.
  - Ensure that the intravenous tubing is compatible with the infusion pump.
  - Use either polyolefin, DEHP-free PVC or EVA intravenous tubing sets.
 |  | Important: Do not use an in-line filter for 72-hour, 96-hour, or 7-day bags.
8. Prime the intravenous tubing only with the solution in the bag containing the FINAL prepared BLINCYTO solution for infusion.
9. Store refrigerated at 2°C to 8°C (36°F to 46°F) if not used immediately [see Dosage and Administration (2.6)].
 | Table 3. For 72-Hour, 96-Hour, and 7-Day Infusion: Patients Weighing 45 kg or More
 | Infusion Duration |  | Dose | Reconstituted BLINCYTO |  |  | Volume of Preservative-Free 0.9% Sodium Chloride Injection, USP needed to q.s. to Final Volume |  | Final Volume of IV Bag
 | Infusion Duration |  | Dose | Volume |  | Vials | Volume of Preservative-Free 0.9% Sodium Chloride Injection, USP needed to q.s. to Final Volume |  | Final Volume of IV Bag
 | 72 hours |  | 28 mcg/day | 8.4 mL |  | 3 |  | 105 mL | 162 mL
 | 96 hours |  | 28 mcg/day | 10.4 mL |  | 4 |  | 130 mL | 200 mL
 | 7 days |  | 28 mcg/day | 16.8 mL |  | 6 |  | 1 mL | 110 mL
 | Table 4. For 72-Hour, 96-Hour, and 7-Day Infusion: Patients Weighing Between 5.4 kg and Less Than 45 kg
 | Infusion Duration |  | Dose | BSA (m^2) |  | Reconstituted BLINCYTO |  | Volume of Preservative-Free 0.9% Sodium Chloride Injection, USP needed to q.s. to Final Volume | Final Volume of IV Bag
 | Infusion Duration |  | Dose | BSA (m^2) |  | Volume | Vials | Volume of Preservative-Free 0.9% Sodium Chloride Injection, USP needed to q.s. to Final Volume | Final Volume of IV Bag
 | 72 hours |  | 15 mcg/m^2/day | 1.5 – 1.59 |  | 6.8 mL | 3 | 107 mL | 162 mL
 | 72 hours |  | 15 mcg/m^2/day | 1.4 – 1.49 |  | 6.4 mL | 3 | 107 mL | 162 mL
 | 72 hours |  | 15 mcg/m^2/day | 1.30 – 1.39 |  | 6 mL | 3 | 108 mL | 162 mL
 | 72 hours |  | 15 mcg/m^2/day | 1.20 – 1.29 |  | 5.4 mL | 2 | 108 mL | 162 mL
 | 72 hours |  | 15 mcg/m^2/day | 1.10 – 1.19 |  | 5 mL | 2 | 109 mL | 162 mL
 | 72 hours |  | 15 mcg/m^2/day | 1 – 1.09 |  | 4.6 mL | 2 | 109 mL | 162 mL
 | 72 hours |  | 15 mcg/m^2/day | 0.9 – 0.99 |  | 4.2 mL | 2 | 110 mL | 162 mL
 | 72 hours |  | 15 mcg/m^2/day | 0.8 – 0.89 |  | 3.8 mL | 2 | 110 mL | 162 mL
 | 72 hours |  | 15 mcg/m^2/day | 0.7 – 0.79 |  | 3.2 mL | 2 | 111 mL | 162 mL
 | 72 hours |  | 15 mcg/m^2/day | 0.6 – 0.69 |  | 2.8 mL | 1 | 111 mL | 162 mL
 | 72 hours |  | 15 mcg/m^2/day | 0.5 – 0.59 |  | 2.3 mL | 1 | 111 mL | 162 mL
 | 72 hours |  | 15 mcg/m^2/day | 0.4 – 0.49 |  | 2 mL | 1 | 112 mL | 162 mL
 | 72 hours |  | 15 mcg/m^2/day | 0.35 – 0.39 |  | 1.7 mL | 1 | 112 mL | 162 mL
 | 72 hours |  | 15 mcg/m^2/day | 0.3 – 0.34 |  | 1.4 mL | 1 | 112 mL | 162 mL
 | 72 hours |  | 15 mcg/m^2/day | 0.25 – 0.29 |  | 1.2 mL | 1 | 113 mL | 162 mL
 | 96 hours |  | 15 mcg/m^2/day | 1.5 – 1.59 |  | 8.4 mL | 3 | 132 mL | 200 mL
 | 96 hours |  | 15 mcg/m^2/day | 1.4 – 1.49 |  | 7.8 mL | 3 | 132 mL | 200 mL
 | 96 hours |  | 15 mcg/m^2/day | 1.30 – 1.39 |  | 7.4 mL | 3 | 133 mL | 200 mL
 | 96 hours |  | 15 mcg/m^2/day | 1.20 – 1.29 |  | 6.8 mL | 3 | 133 mL | 200 mL
 | 96 hours |  | 15 mcg/m^2/day | 1.10 – 1.19 |  | 6.2 mL | 3 | 134 mL | 200 mL
 | 96 hours |  | 15 mcg/m^2/day | 1 – 1.09 |  | 5.6 mL | 2 | 134 mL | 200 mL
 | 96 hours |  | 15 mcg/m^2/day | 0.9 – 0.99 |  | 5.2 mL | 2 | 135 mL | 200 mL
 | 96 hours |  | 15 mcg/m^2/day | 0.8 – 0.89 |  | 4.6 mL | 2 | 135 mL | 200 mL
 | 96 hours |  | 15 mcg/m^2/day | 0.7 – 0.79 |  | 4 mL | 2 | 136 mL | 200 mL
 | 96 hours |  | 15 mcg/m^2/day | 0.6 – 0.69 |  | 3.4 mL | 2 | 137 mL | 200 mL
 | 96 hours |  | 15 mcg/m^2/day | 0.5 – 0.59 |  | 2.8 mL | 1 | 137 mL | 200 mL
 | 96 hours |  | 15 mcg/m^2/day | 0.4 – 0.49 |  | 2.4 mL | 1 | 138 mL | 200 mL
 | 96 hours |  | 15 mcg/m^2/day | 0.35 – 0.39 |  | 2.1 mL | 1 | 138 mL | 200 mL
 | 96 hours |  | 15 mcg/m^2/day | 0.3 – 0.34 |  | 1.8 mL | 1 | 138 mL | 200 mL
 | 96 hours |  | 15 mcg/m^2/day | 0.25 – 0.29 |  | 1.5 mL | 1 | 139 mL | 200 mL
 | 7 days |  | 15 mcg/m^2/day | 1.5 – 1.59 |  | 14 mL | 5 | 3.8 mL | 110 mL
 | 7 days |  | 15 mcg/m^2/day | 1.4 – 1.49 |  | 13.1 mL | 5 | 4.7 mL | 110 mL
 | 7 days |  | 15 mcg/m^2/day | 1.30 – 1.39 |  | 12.2 mL | 5 | 5.6 mL | 110 mL
 | 7 days |  | 15 mcg/m^2/day | 1.20 – 1.29 |  | 11.3 mL | 5 | 6.5 mL | 110 mL
 | 7 days |  | 15 mcg/m^2/day | 1.10 – 1.19 |  | 10.4 mL | 4 | 7.4 mL | 110 mL
 | 7 days |  | 15 mcg/m^2/day | 1 – 1.09 |  | 9.5 mL | 4 | 8.3 mL | 110 mL
 | 7 days |  | 15 mcg/m^2/day | 0.9 – 0.99 |  | 8.6 mL | 4 | 9.2 mL | 110 mL
 | 7 days |  | 15 mcg/m^2/day | 0.8 – 0.89 |  | 7.7 mL | 3 | 10.1 mL | 110 mL
 | 7 days |  | 15 mcg/m^2/day | 0.7 – 0.79 |  | 6.8 mL | 3 | 11 mL | 110 mL
 | 7 days |  | 15 mcg/m^2/day | 0.6 – 0.69 |  | 5.9 mL | 3 | 11.9 mL | 110 mL
 | 7 days |  | 15 mcg/m^2/day | 0.5 – 0.59 |  | 5 mL | 2 | 12.8 mL | 110 mL
 | 7 days |  | 15 mcg/m^2/day | 0.4 – 0.49 |  | 4.1 mL | 2 | 13.7 mL | 110 mL
 | 7 days |  | 15 mcg/m^2/day | 0.35 – 0.39 |  | 3.4 mL | 2 | 14.4 mL | 110 mL
 | 7 days |  | 15 mcg/m^2/day | 0.3 – 0.34 |  | 2.8 mL | 1 | 15 mL | 110 mL
 | 7 days |  | 15 mcg/m^2/day | 0.25 – 0.29 |  | 2.5 mL | 1 | 15.3 mL | 110 mL
The administration of BLINCYTO as a 72-hour, 96-hour, and 7-day infusion is not recommended for patients weighing less than 5.4 kg.
Administration of BLINCYTO: 72-Hour, 96-Hour, or 7-Day Intravenous Bag
- Administer BLINCYTO as a continuous intravenous infusion at a constant flow rate using an infusion pump. The pump should be programmable, lockable, non-elastomeric, and have an alarm.
- The final volume of infusion solution will be more than the volume administered to the patient to account for the priming of the intravenous tubing and to ensure that the patient will receive the full dose of BLINCYTO.
  - For 72-hour infusion (162 mL) will be more than the volume administered to the patient (130 mL).
  - For 96-hour infusion (200 mL) will be more than the volume administered to the patient (173 mL).
  - For 7-day infusion (110 mL) will be more than the volume administered to the patient (100 mL).
- Ensure that the intravenous tubing is primed only with the solution in the bag containing the FINAL prepared BLINCYTO solution for infusion.
- Do not use an in-line filter for 72-hour, 96-hour, or 7-day bags.
- Infuse the FINAL prepared BLINCYTO infusion solution according to the instructions on the pharmacy label on the prepared bag at one of the following constant infusion rates:
  - Infusion rate of 1.8 mL/hour for a duration of 72 hours or 96 hours, OR
  - Infusion rate of 0.6 mL/hour for a duration of 7 days.
- Important Note: Do not flush the BLINCYTO infusion line, especially when changing infusion bags. Flushing when changing bags or at completion of infusion can result in excess dosage and complications thereof. When administering via a multi-lumen venous catheter, infuse BLINCYTO through a dedicated lumen. Before flushing the catheter system, residual amounts of BLINCYTO must be aspirated from the catheter system to avoid bolus administration.
- At the end of the infusion, any remaining solution in the intravenous bag and intravenous tubing should be discarded in accordance with local requirements.

Manufactured by:
Amgen Inc.
One Amgen Center Drive
Thousand Oaks, California 91320-1799
U.S. License No. 1080

BLINCYTO® (blinatumomab)

Patent: http://pat.amgen.com/blincyto/

© 2024 Amgen Inc. All rights reserved.
V2

Revised: 12/2024

PRINCIPAL DISPLAY PANEL - Kit Package

AMGEN®

35
mcg/vial

1 BLINCYTO® Single-Dose Vial
1 IV Solution Stabilizer Vial

NDC 55513-160-01

BLINCYTO®
(blinatumomab)
for Injection

35 mcg/vial

For Intravenous Infusion Only
Store refrigerated at 2°C to 8°C (36°F to 46°F).
Store in carton to protect from light.
DO NOT SHAKE reconstituted solution.
Dispense the enclosed Medication Guide to each patient.

No Preservative
Single-Dose Vial –
Discard unused portion.

Rx Only